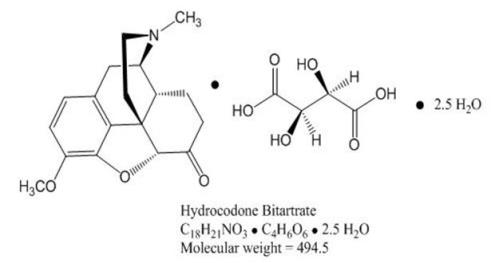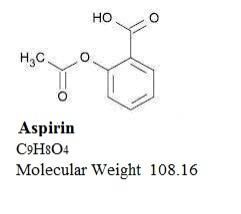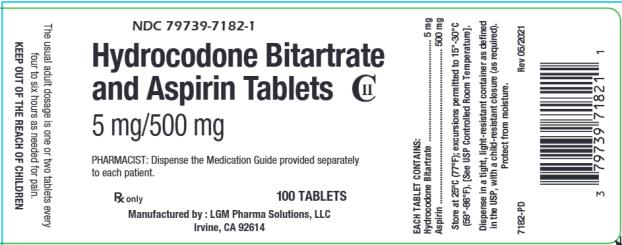 DRUG LABEL: Hydrocodone Bitartrate and Aspirin
NDC: 79739-7182 | Form: TABLET
Manufacturer: LGM PHARMA SOLUTIONS, LLC
Category: prescription | Type: HUMAN PRESCRIPTION DRUG LABEL
Date: 20240327
DEA Schedule: CII

ACTIVE INGREDIENTS: HYDROCODONE BITARTRATE 5 mg/1 1; ASPIRIN 500 mg/1 1
INACTIVE INGREDIENTS: MICROCRYSTALLINE CELLULOSE; ANHYDROUS LACTOSE; HYDROXYPROPYL CELLULOSE (90000 WAMW); CROSPOVIDONE (12 MPA.S AT 5%); STEARIC ACID; SILICON DIOXIDE; TALC; STARCH, CORN

Hydrocodone Bitartrate with Aspirin

HYDROCODONE BITARTRATE and ASPIRIN TABLETS CII

Revised: January 2024

WARNING: SERIOUS AND LIFE-THREATENING RISKS FROM USE OF HYDROCODONE BITARTRATE AND ASPIRIN TABLETS

Addition, Abuse and Misuse

Because the use of Hydrocodone Bitartrate and Aspirin Tablets exposes patients and other users to the risks of opioid addiction, abuse, and misuse, which can lead to overdose and death, assess each patient’s risk prior to prescribing and reassess all patients regularly for the development of these behaviors and conditions [see Warnings].

Life-Threatening Respiratory Depression

Serious, life-threatening, or fatal respiratory depression may occur with use of Hydrocodone Bitartrate and Aspirin Tablets, especially during initiation or following a dosage increase. To reduce the risk of respiratory depression, proper dosing and titration of Hydrocodone Bitartrate and Aspirin Tablets are essential [see Warnings].

Accidental Ingestion

Accidental ingestion of even one dose of Hydrocodone Bitartrate and Aspirin Tablets, especially by children, can result in a fatal overdose of hydrocodone [see Warnings].

Risks From Concomitant Use With Benzodiazepines Or Other CNS Depressants

Concomitant use of opioids with benzodiazepines or other central nervous system (CNS) depressants, including alcohol, may result in profound sedation, respiratory depression, coma, and death. Reserve concomitant prescribing of Hydrocodone Bitartrate and Aspirin Tablets and benzodiazepines or other CNS depressants for use in patients for whom alternative treatment options are inadequate [see Warnings, Precautions; Drug Interactions].

Neonatal Opioid Withdrawal Syndrome (NOWS)

If opioid use is required for an extended period of time in a pregnant woman, advise the patient of the risk of NOWS, which may be life-threatening if not recognized and treated. Ensure that management by neonatology experts will be available at delivery [see Warnings].

Opioid Analgesic Risk Evaluation and Mitigation Strategy (REMS)

Healthcare providers are strongly encouraged to complete a REMS complaint education program and to counsel patients and caregivers on serious risks, safe use, and the importance of reading the Medication Guide with each prescription [see Warnings].

Cytochrome P450 3A4 Interaction

The concomitant use of Hydrocodone Bitartrate and Aspirin Tablets with all Cytochrome P450 3A4 inhibitors may result in an increase in hydrocodone plasma concentrations, which could increase or prolong adverse reactions and may cause potentially fatal respiratory depression. In addition, discontinuation of a concomitantly used Cytochrome P450 3A4 inducer may result in an increase in hydrocodone plasma concentrations. Monitor patients receiving Hydrocodone Bitartrate and Aspirin Tablets and any Cytochrome P450 3A4 inhibitor or inducer for signs of respiratory depression or sedation [see CLINICAL PHARMACOLOGY, WARNINGS, PRECAUTIONS; Drug Interactions].

DESCRIPTION

Hydrocodone Bitartrate and Aspirin Tablets are immediate-release tablets for oral administration only.

Each Hydrocodone Bitartrate and Aspirin Tablet, 5 mg/500 mg contains:

Hydrocodone Bitartrate ……………….. 5 mg

Aspirin ……………………………................ 500 mg

Hydrocodone Bitartrate is an opioid agonist and occurs as fine, white crystals or as a crystalline powder. It is affected by light. It is soluble in water, slightly soluble in alcohol, and insoluble in ether and chloroform. The chemical name is: 4,5α-epoxy-3-methoxy-17-methylmorphinan-6-one tartrate (1:1) hydrate (2:5). It has the following structural formula:

Aspirin, acetylsalicylic acid, is a nonsteroidal anti-inflammatory drug which is an odorless white, needle-like crystalline or powdery substance. The aspirin component is 2-(acetyloxy)-, Benzoic acid. When exposed to moisture, aspirin hydrolyzes into salicylic and acetic acids, and gives off a vinegary-odor. It is highly lipid soluble and slightly soluble in water; freely soluble in alcohol; soluble in chloroform and in ether; sparingly soluble in absolute ether. Its structure is as follows:

In addition, each tablet contains the following inactive ingredients: Microcrystalline Cellulose, Anhydrous Lactose, Corn Starch, Hypromellose, Crospovidone, Stearic Acid, Talc, Colloidal Silicon Dioxide.

CLINICAL PHARMACOLOGY

Mechanism of Action

Hydrocodone is full opioid agonist with relative selectivity for the mu-opioid (μ) receptor, although it can interact with other opioid receptors at higher doses. The principal therapeutic action of hydrocodone is analgesia. Like all full opioid agonists, there is no ceiling effect for analgesia with hydrocodone. Clinically, dosage is titrated to provide adequate analgesia and may be limited by adverse reactions, including respiratory and CNS depression.

The precise mechanism of the analgesic action is unknown. However, specific CNS opioid receptors for endogenous compounds with opioid-like activity have been identified throughout the brain and spinal cord and are thought to play a role in the analgesic effects of this drug.

Aspirin is a nonsteroidal anti-inflammatory drug. Aspirin (acetylsalicylic acid) is a more potent inhibitor of both prostaglandin synthesis and platelet aggregation than other salicylic acid derivatives. The differences in activity between aspirin and salicylic acid are thought to be due to the acetyl group on the aspirin molecule. This acetyl group is responsible for the inactivation of cyclo-oxygenase via acetylation.

Aspirin (acetylsalicylic acid) works by inhibiting the body's production of prostaglandins, including prostaglandins involved in inflammation. Prostaglandins cause pain sensations by stimulating muscle contractions and dilating blood vessels throughout the body. In the CNS, aspirin works on the hypothalamus heat-regulating center to reduce fever, however, other mechanisms may be involved.

Pharmacodynamics

Aspirin affects platelet aggregation by irreversibly inhibiting prostaglandin cyclo-oxygenase. This effect lasts for the life of the platelet and prevents the formation of the platelet aggregating factor thromboxane A2. Nonacetylated salicylates do not inhibit this enzyme and have no effect on platelet aggregation. At somewhat higher doses, aspirin reversibly inhibits the formation of prostaglandin I2 (prostacyclin), which is an arterial vasodilator and inhibits platelet aggregation.

At higher doses aspirin is an effective anti-inflammatory agent, partially due to inhibition of inflammatory mediators via cyclo-oxygenase inhibition in peripheral tissues. In vitro studies suggest that other mediators of inflammation may also be suppressed by aspirin administration, although the precise mechanism of action has not been elucidated. It is this nonspecific suppression of cyclo-oxygenase activity in peripheral tissues following large doses that leads to its primary side effect of gastric irritation. [see ADVERSE REACTIONS].

Effects on the Central Nervous System

Hydrocodone produces respiratory depression by direct action on brain stem respiratory centers. The respiratory depression involves a reduction in the responsiveness of the brain stem respiratory centers to both increases in carbon dioxide tension and electrical stimulation.

Hydrocodone causes miosis, even in total darkness. Pinpoint pupils are a sign of opioid overdose but are not pathognomonic (e.g., pontine lesions of hemorrhagic or ischemic origins may produce similar findings). Marked mydriasis rather than miosis may be seen due to hypoxia in overdose situations.

Effects on the Gastrointestinal Tract and Other Smooth Muscle

Hydrocodone causes a reduction in motility associated with an increase in smooth muscle tone in the antrum of the stomach and duodenum. Digestion of food in the small intestine is delayed and propulsive contractions are decreased. Propulsive peristaltic waves in the colon are decreased, while tone may be increased to the point of spasm, resulting in constipation. Other opioid-induced effects may include a reduction in biliary and pancreatic secretions, spasm of sphincter of Oddi, and transient elevations in serum amylase.

Aspirin can produce gastrointestinal injury (lesions, ulcers) through a mechanism that is not yet completely understood, but may involve a reduction in eicosanoid synthesis by the gastric mucosa. Decreased production of prostaglandins may compromise the defenses of the gastric mucosa and the activity of substances involved in tissue repair and ulcer healing.

Effects on the Cardiovascular System

Hydrocodone produces peripheral vasodilation which may result in orthostatic hypotension or syncope. Manifestations of histamine release and/or peripheral vasodilation may include pruritus, flushing, red eyes, sweating, and/or orthostatic hypotension.

Effects on the Endocrine System

Opioids inhibit the secretion of adrenocorticotropic hormone (ACTH), cortisol, and luteinizing hormone (LH) in humans [see ADVERSE REACTIONS]. They also stimulate prolactin, growth hormone (GH) secretion, and pancreatic secretion of insulin and glucagon.

Use of opioids for an extended period of time may influence the hypothalamic-pituitary-gonadal axis, leading to androgen deficiency that may manifest as symptoms as low libido, impotence, erectile dysfunction, amenorrhea, or infertility. The casual role of opioids in the syndrome of hypogonadism is unknown because the various medical, physical, lifestyle, and psychological stressors that may influence gonadal hormone levels have not been adequately controlled for in studies conducted to date [see ADVERSE REACTIONS].

Effects on the Immune System

Opioids have been shown to have a variety of effects on components of the immune system. The clinical significance of these findings is unknown. Overall, the effects of opioids appear to be modestly immunosuppressive.

Concentration-Efficacy Relationships

The minimum effective analgesic concentration will vary widely among patients, especially among patients who have been previously treated with agonist opioid agonists. The minimum effective analgesic concentration of hydrocodone for any individual patient may increase over time due to an increase in pain, the development of a new pain syndrome, and/or the development of analgesic tolerance [see DOSAGE AND ADMINISTRATION].

Concentration-Adverse Reaction Relationships

There is a relationship between increasing hydrocodone plasma concentration and increasing frequency of dose-related opioid adverse reactions such as nausea, vomiting, CNS effects, and respiratory depression. In opioid-tolerant patients, the situation may be altered by the development of tolerance to opioid-related adverse reactions [see DOSAGE AND ADMINISTRATION].

The dose of Hydrocodone Bitartrate and Aspirin Tablets must be individualized because the effective analgesic dose for some patients will be too high to be tolerated by other patients [see DOSAGE AND ADMINISTRATION].

Pharmacokinetics

The behavior of the individual components is described below.

Hydrocodone

Absorption:

Following a 10 mg oral dose of hydrocodone administered to five adult male subjects, the mean peak concentration was 23.6 ± 5.2 ng/mL. Maximum serum levels were achieved at 1.3 ± 0.3 hours and the half-life was determined to be 3.8 ± 0.3 hours.

Elimination:

Metabolism

Hydrocodone exhibits a complex pattern of metabolism including O-demethylation, N-demethylation and 6-keto reduction to the corresponding 6-α- and 6-β-hydroxymetabolites. CYP3A4 mediated N-demethylation to norhydrocodone is the primary metabolic pathway of hydrocodone with a lower contribution from CYP2D6 mediated O-demethylation to hydromorphone. Hydromorphone is formed from the O-demethylation of hydrocodone and may contribute to the total analgesic effect of hydrocodone. Therefore, the formation of these and related metabolites can, in theory, be affected by other drugs [see PRECAUTIONS; Drug Interactions]. N-demethylation of hydrocodone to form norhydrocodone via CYP3A4 while O-demethylation of hydrocodone to hydromorphone is predominantly catalyzed by CYP2D6 and to a lesser extent by an unknown low affinity CYP enzyme.

Excretion

Hydrocodone and its metabolites are eliminated primarily in the kidneys.

Aspirin

Absorption:

In general, immediate release aspirin is well and completely absorbed from the gastrointestinal (GI) tract. Following absorption, aspirin is hydrolyzed to salicylic acid with peak plasma levels of salicylic acid occurring within 1-2 hours of dosing [see Pharmacokinetics—Metabolism]. The rate of absorption from the GI tract is dependent upon the dosage form, the presence or absence of food, gastric pH (the presence or absence of GI antacids or buffering agents), and other physiologic factors.

Distribution:

Salicylic acid is widely distributed to all tissues and fluids in the body including the central nervous system (CNS), breast milk, and fetal tissues. The highest concentrations are found in the plasma, liver, renal cortex, heart, and lungs. The protein binding of salicylate is concentration-dependent, i.e., nonlinear. At low concentrations (<100 micrograms/milliliter ([micro]g/mL)), approximately 90 percent of plasma salicylate is bound to albumin while at higher concentrations (>400 [micro]g/mL), only about 75 percent is bound.

Elimination:

Metabolism

Aspirin is rapidly hydrolyzed in the plasma to salicylic acid such that plasma levels of aspirin are essentially undetectable 1-2 hours after dosing. Salicylic acid is primarily conjugated in the liver to form salicyluric acid, a phenolic glucuronide, an acyl glucuronide, and a number of minor metabolites. Salicylic acid has a plasma half-life of approximately 6 hours. Salicylate metabolism is saturable and total body clearance decreases at higher serum concentrations due to the limited ability of the liver to form both salicyluric acid and phenolic glucuronide. Following toxic doses (10-20 grams (g)), the plasma half-life may be increased to over 20 hours.

Excretion

The elimination of salicylic acid follows zero order pharmacokinetics; (i.e., the rate of drug elimination is constant in relation to plasma concentration). Renal excretion of unchanged drug depends upon urine pH. As urinary pH rises above 6.5, the renal clearance of free salicylate increases from <5 percent to >80 percent. Following therapeutic doses, approximately 10 percent is found excreted in the urine as salicylic acid, 75 percent as salicyluric acid, and 10 percent phenolic and 5 percent acyl glucuronides of salicylic acid.

INDICATIONS AND USAGE

Hydrocodone Bitartrate and Aspirin Tablets are indicated for the management of pain severe enough to require an opioid analgesic and for which alternative treatments are inadequate.

Limitations of Use

Because of the risks of addiction, abuse, and misuse, with opioids, which can occur at any dosage or duration, reserve Hydrocodone Bitartrate and Aspirin Tablets for use in patients for whom alternative treatment options (e.g., non-opioid analgesics):

- have not been tolerated or are not expected to be tolerated.
- have not provided adequate analgesia or are not expected to provide adequate analgesia.

Hydrocodone Bitartrate and Aspirin Tablets should not be used for extended period of time unless the pain remains severe enough to require an opioid analgesic and for which alternative treatment options continue to be inadequate.

CONTRADICTIONS

Hydrocodone Bitartrate and Aspirin Tablets are contraindicated in patients with:

- Significant respiratory depression [see WARNINGS]
- Acute or severe bronchial asthma in an unmonitored setting or in the absence of resuscitative equipment [see WARNINGS]
- Known or suspected gastrointestinal obstruction, including paralytic ileus [see WARNINGS]
- Hypersensitivity to hydrocodone or aspirin (e.g., angioedema) [see WARNINGS]
- Hemophilia [see WARNINGS]
- Aspirin should not be used in children or teenagers for viral infections, with or without fever, because of the risk of Reye’s syndrome with concomitant use of aspirin in certain viral illnesses [see WARNINGS]
- Known allergy to nonsteroidal anti-inflammatory drugs (NSAIDs) [see WARNINGS, PRECAUTIONS]
- Syndrome of asthma, rhinitis, and nasal polyps [see WARNINGS, PRECAUTIONS]

WARNINGS

Addiction, Abuse, Misuse

Hydrocodone Bitartrate and Aspirin Tablets contain hydrocodone, a Schedule II controlled substance. As an opioid, Hydrocodone Bitartrate and Aspirin Tablets expose users to the risks of addiction, abuse, and misuse [see DRUG ABUSE AND DEPENDENCE].

Although the risk of addiction in any individual is unknown, it can occur in patients appropriately prescribed Hydrocodone Bitartrate and Aspirin Tablets. Addiction can occur at recommended dosages and if the drug is misused or abused.

Assess each patient's risk for opioid addiction, abuse, or misuse prior to prescribing Hydrocodone Bitartrate and Aspirin Tablets, and reassess all patients receiving Hydrocodone Bitartrate and Aspirin Tablets for the development of these behaviors and conditions. Risks are increased in patients with a personal or family history of substance abuse (including drug or alcohol abuse or addiction) or mental illness (e.g., major depression). The potential for these risks should not, however, prevent the proper management of pain in any given patient. Patients at increased risk may be prescribed opioids such as Hydrocodone Bitartrate and Aspirin Tablets, but use in such patients necessitates intensive counseling about the risks and proper use of Hydrocodone Bitartrate and Aspirin Tablets along with frequent reevaluation for signs of addiction, abuse, and misuse. Consider prescribing naloxone for the emergency treatment of opioid overdose [see WARNINGS; Life-Threatening Respiratory Depression, DOSAGE AND ADMINISTRATION; Patient Access to Naloxone for the Emergency Treatment of Opioid Overdose].

Opioids are sought for nonmedical use and are subject to diversion from legitimate prescribed use. Consider these risks when prescribing or dispensing Hydrocodone Bitartrate and Aspirin Tablets. Strategies to reduce these risks include prescribing the drug in the smallest appropriate quantity and advising the patient on careful storage of the drug during the course of treatment and proper disposal of unused drug. Contact local state professional licensing board or state-controlled substances authority for information on how to prevent and detect abuse or diversion of this product.

Life-Threatening Respiratory Depression

Serious, life-threatening, or fatal respiratory depression has been reported with the use of opioids, even when used as recommended. Respiratory depression, if not immediately recognized and treated, may lead to respiratory arrest and death. Management of respiratory depression may include close observation, supportive measures, and use of opioid antagonists, depending on the patient's clinical status [see OVERDOSAGE]. Carbon dioxide (CO2) retention from opioid-induced respiratory depression can exacerbate the sedating effects of opioids.

While serious, life-threatening, or fatal respiratory depression can occur at any time during the use of Hydrocodone Bitartrate and Aspirin Tablets, the risk is greatest during the initiation of therapy or following a dosage increase.

To reduce the risk of respiratory depression, proper dosing and titration of Hydrocodone Bitartrate and Aspirin Tablets are essential [see DOSAGE AND ADMINISTRATION]. Overestimating the Hydrocodone Bitartrate and Aspirin Tablets dosage when converting patients from another opioid product can result in a fatal overdose.

Accidental ingestion of Hydrocodone Bitartrate and Aspirin Tablets, especially by children, can result in respiratory depression and death due to an overdose of Hydrocodone Bitartrate and Aspirin Tablets.

Educate patients and caregivers on how to recognize respiratory depression and emphasize the importance of calling 911 or getting emergency medical help right away in the event of a known or suspected overdose [see PRECAUTIONS; Information for Patients/Caregivers].

Opioids can cause sleep-related breathing disorders including central sleep apnea (CSA) and sleep-related hypoxemia. Opioid use increases the risk of CSA in a dose-dependent fashion. In patients who present with CSA, consider decreasing the opioid dosage using best practices for opioid taper [see DOSAGE AND ADMINISTRATION].

Patient Access to Naloxone for the Emergency Treatment of Opioid Overdose

Discuss the availability of naloxone for the emergency treatment of opioid overdose with the patient and caregiver and assess the potential need for personal access to naloxone, both when initiating and renewing treatment with Hydrocodone Bitartrate and Aspirin Tablets. Inform patients and caregivers about the various ways to obtain naloxone as permitted by individual state naloxone dispensing and prescribing requirements or guidelines (e.g., by prescription, directly from a pharmacist, or as part of a community-based program). Educate patients and caregivers on how to recognize respiratory depression and emphasize the importance of calling 911 or getting emergency medical help, even if naloxone is administered [see PRECAUTIONS; Information for Patients/Caregivers].

Consider prescribing naloxone, based on the patient’s risk factors for overdose, such as concomitant use of CNS depressants, a history of opioid use disorder, or prior opioid overdose. The presence of risk factors for overdose should not prevent the proper management of pain in any given patient. Also consider prescribing naloxone when there are household members (including children) or other close contacts at risk for accidental ingestion or overdose. If naloxone is prescribed, educate patients and caregivers on how to treat with naloxone [see DOSAGE AND ADMINISTRATION, WARNINGS, OVERDOSAGE].

Risks from Concomitant Use with Benzodiazepines or Other CNS Depressants

Profound sedation, respiratory depression, coma, and death may result from the concomitant use of Hydrocodone Bitartrate and Aspirin Tablets with benzodiazepines and/or other CNS depressants, including alcohol (e.g., non-benzodiazepine sedatives/hypnotics, anxiolytics, tranquilizers, muscle relaxants, general anesthetics, antipsychotics, other opioids). Because of these risks, reserve concomitant prescribing of these drugs for use in patients for whom alternative treatment options are inadequate.

Observational studies have demonstrated that concomitant use of opioid analgesics and benzodiazepines increases the risk of drug-related mortality compared to use of opioid analgesics alone. Because of similar pharmacological properties, it is reasonable to expect similar risk with the concomitant use of other CNS depressant drugs with opioid analgesics [see PRECAUTIONS; Drug Interactions].

If the decision is made to prescribe a benzodiazepine or other CNS depressant concomitantly with an opioid analgesic, prescribe the lowest effective dosages and minimum durations of concomitant use. In patients already receiving an opioid analgesic, prescribe a lower initial dose of the benzodiazepine or other CNS depressant than indicated in the absence of an opioid, and titrate based on clinical response. If an opioid analgesic is initiated in a patient already taking a benzodiazepine or other CNS depressant, prescribe a lower initial dose of the opioid analgesic, and titrate based on clinical response. Inform patients and caregivers of this potential interaction and educate them on the signs and symptoms of respiratory depression (including sedation). If concomitant use is warranted, consider prescribing naloxone for the emergency treatment of opioid overdose [see DOSAGE AND ADMINISTRATION; Patient Access to Naloxone for the Emergency Treatment of Opioid Overdose, WARNINGS; Life-Threatening Respiratory Depression].

Advise both patients and caregivers about the risks of respiratory depression and sedation when Hydrocodone Bitartrate and Aspirin Tablets are used with benzodiazepines or other CNS depressants (including alcohol and illicit drugs). Advise patients not to drive or operate heavy machinery until the effects of concomitant use of the benzodiazepine or other CNS depressant have been determined. Screen patients for risk of substance use disorders, including opioid abuse and misuse, and warn them of the risk for overdose and death associated with the use of additional CNS depressants including alcohol and illicit drugs [ see PRECAUTIONS; Drug Interactions; Information for Patients/Caregivers].

Neonatal Opioid Withdrawal Syndrome

Use of Hydrocodone Bitartrate and Aspirin Tablets for an extended period of time during pregnancy can result in withdrawal in the neonate. Neonatal opioid withdrawal syndrome, unlike opioid withdrawal syndrome in adults, may be life-threatening if not recognized and treated, and requires management according to protocols developed by neonatology experts. Observe newborns for signs of neonatal opioid withdrawal syndrome and manage accordingly. Advise pregnant women using opioids for an extended period of time of the risk of neonatal opioid withdrawal syndrome and ensure that appropriate treatment will be available [see PRECAUTIONS; Information for Patients/Caregivers; Pregnancy].

Opioid Analgesic Risk Evaluation and Mitigation Strategy (REMS)

To ensure that the benefits of opioids analgesics outweigh the risks of addition, abuse, and misuse, the Food and Drug Administration (FDA) has required Risk Evaluation and Mitigation Strategy (REMS) for these products. Under the requirements of the REMS, drug companies with approved opioid analgesic products must make REMS-compliant education programs available to healthcare providers. Prescribers are strongly encouraged to do all of the following:

- Complete a REMS-compliant education program offered by and accredited provider of continuing education (CE) or another education program that includes all the elements of the FDA Education Blueprint for Heath Care Providers Involved in the Management or Support of Patients with Pain.
- Discuss the safe use, serious risks, and proper storage and disposal of opioid analgesics with patients and/or their caregivers every time these medicines are prescribed. The Patient Counseling Guide (PCG) can be obtained at this link: www.fda.gov/OpioidAnalgesicREMSPCG.
- Emphasize to patients and their caregivers the importance of reading the Medication Guide that they will receive from their pharmacist every time an opioid analgesic is dispensed to them.
- Consider using other tools to improve patient, household, and community safety, such as patient-prescriber agreements that reinforce patient-prescriber responsibilities.

To obtain further information on the opioid analgesic REMS and for a list of accredited REMS CME/CE, call 1-800-503-0784, or log on to www.opioidanalgesicrems.com. The FDA Blueprint can be found at www.fda.gov/OpioidAnalgesicREMSBlueprint.

Risks of Concomitant Use for Discontinuation of Cytochrome P450 3A4 Inhibitors and Inducers

Concomitant use of Hydrocodone Bitartrate and Aspirin Tablets with a CYP3A4 inhibitor, such as macrolide antibiotics (e.g., erythromycin), azole-antifungal agents (e.g., ketoconazole), and protease inhibitors (e.g., ritonavir), may increase plasma concentrations of Hydrocodone Bitartrate and Aspirin Tablets and prolong opioid adverse reactions, and which may cause potentially fatal respiratory depression [see WARNINGS], particularly when an inhibitor is added after a stable dose of Hydrocodone Bitartrate and Aspirin Tablets is achieved. Similarly, discontinuation of a CYP3A4 inducer, such as rifampin, carbamazepine, and phenytoin, in Hydrocodone Bitartrate and Aspirin Tablet-treated patients, evaluate patients at frequent intervals and consider dosage reduction of Hydrocodone Bitartrate and Aspirin Tablets until stable drug effects are achieved [see PRECAUTIONS; Drug Interactions].

Concomitant use of Hydrocodone Bitartrate and Aspirin Tablets with CYP3A4 inducers or discontinuation of a CYP3A4 inhibitor could decrease hydrocodone plasma concentrations, decrease opioid efficacy or, possibly, lead to a withdrawal syndrome in a patient who had developed physical dependence to hydrocodone. When using Hydrocodone Bitartrate and Aspirin Tablets with CYP3A4 inducers or discontinuing CYP3A4 inhibitors, monitor patients closely at frequent intervals and consider increasing the opioid dosage if needed to maintain adequate analgesia or if symptoms of opioid withdrawal occur [see PRECAUTIONS; Drug Interactions].

Opioid-Induced Hyperalgesia and Allodynia

Opioid-Induced Hyperalgesia (OIH) occurs when an opioid analgesic paradoxically causes an increase in pain, or an increase in sensitivity to pain. This condition differs from tolerance, which is the need for increasing doses of opioids to maintain a defined effect [see Dependence]. Symptoms of OIH include (but may not be limited to) increased levels of pain upon opioid dosage increase, decreased levels of pain upon opioid dosage decrease, or pain from ordinarily non-painful stimuli (allodynia). These symptoms may suggest OIH only if there is no evidence of underlying disease progression, opioid tolerance, opioid withdrawal, or addictive behavior.

Cases of OIH have been reported, both with short-term and longer-term use of opioid analgesics. Though the mechanism of OIH is not fully understood, multiple biochemical pathways have been implicated. Medical literature suggests a strong biologic plausibility between opioid analgesics and OIH and allodynia. If a patient is suspected to be experiencing OIH, carefully consider appropriately decreasing the dose of the current opioid analgesic or opioid rotation (safety switching the patient to a different opioid moiety) [see Dosage and Administration; Warnings].

Life-Threatening Respiratory Depression in Patients with Chronic Pulmonary Disease or in Elderly, Cachectic, or Debilitated Patients

The use of Hydrocodone Bitartrate and Aspirin Tablets in patients with acute or severe bronchial asthma in an unmonitored setting or in the absence of resuscitative equipment is contraindicated.

Patients with Chronic Pulmonary Disease: Hydrocodone Bitartrate and Aspirin Tablet-treated patients with significant chronic obstructive pulmonary disease or cor pulmonale, and those with a substantially decreased respiratory reserve, hypoxia, hypercapnia, or pre-existing respiratory depression are at increased risk of decreased respiratory drive including apnea, even at recommended dosages of Hydrocodone Bitartrate and Aspirin Tablets [see WARNINGS; Life-Threatening Respiratory Depression].

Elderly, Cachectic, or Debilitated Patients: Life-threatening respiratory depression is more likely to occur in elderly, cachectic, or debilitated patients because they may have altered pharmacokinetics or altered clearance compared to younger, healthier patients [see WARNINGS; Life-Threatening Respiratory Depression].

Regularly evaluate patients, particularly when initiating and titrating Hydrocodone Bitartrate and Aspirin Tablets and when Hydrocodone Bitartrate and Aspirin Tablets is given concomitantly with other drugs that depress respiration [see WARNINGS; Drug Interactions]. Alternatively, consider the use of non-opioid analgesics in these patients.

Adrenal Insufficiency

Cases of adrenal insufficiency have been reported with opioid use, more often following greater than one month of use. Presentation of adrenal insufficiency may include non-specific symptoms and signs including nausea, vomiting, anorexia, fatigue, weakness, dizziness, and low blood pressure. If adrenal insufficiency is suspected, confirm the diagnosis with diagnostic testing as soon as possible. If adrenal insufficiency is diagnosed, treat with physiologic replacement doses of corticosteroids. Wean the patient off of the opioid to allow adrenal function to recover and continue corticosteroid treatment until adrenal function recovers. Other opioids may be tried as some cases reported use of a different opioid without recurrence of adrenal insufficiency. The information available does not identify any particular opioids as being more likely to be associated with adrenal insufficiency.

Severe Hypotension

Hydrocodone Bitartrate and Aspirin Tablets may cause severe hypotension including orthostatic hypotension and syncope in ambulatory patients. There is increased risk in patients whose ability to maintain blood pressure has already been compromised by a reduced blood volume or concurrent administration of certain CNS depressant drugs (e.g., phenothiazines or general anesthetics) [see PRECAUTIONS; Drug Interactions]. Regularly evaluate these patients for signs of hypotension after initiating or titrating the dosage of Hydrocodone Bitartrate and Aspirin Tablets. In patients with circulatory shock Hydrocodone Bitartrate and Aspirin Tablets may cause vasodilatation that can further reduce cardiac output and blood pressure. Avoid the use of Hydrocodone Bitartrate and Aspirin Tablets with circulatory shock.

Risk of Use in Patients with Increased Intracranial Pressure, Brain Tumors, Head Injury, or Impaired Consciousness

In patients who may be susceptible to the intracranial effects of CO2 retention (e.g., those with evidence of increased intracranial pressure or brain tumors), Hydrocodone Bitartrate and Aspirin Tablets may reduce respiratory drive, and the resultant CO2 retention can further increase intracranial pressure. Monitor such patients for signs of sedation and respiratory depression, particularly when initiating therapy with Hydrocodone Bitartrate and Aspirin Tablets.

Opioids may also obscure the clinical course in a patient with a head injury. Avoid the use of Hydrocodone Bitartrate and Aspirin Tablets in patients with impaired consciousness or coma.

Risks of Use in Patients with Gastrointestinal Conditions

Hydrocodone Bitartrate and Aspirin Tablets are contraindicated in patients with gastrointestinal obstruction, including paralytic ileus.

Hydrocodone may cause spasm of the sphincter of Oddi. Opioids may cause increases in serum amylase. Regulatory evaluate patients with biliary tract disease, including acute pancreatitis, for worsening symptoms.

Gastrointestinal Bleeding, Ulceration, and Perforation

The aspirin in Hydrocodone Bitartrate and Aspirin Tablets can cause GI side effects including stomach pain, heartburn, nausea, vomiting, and gross GI bleeding. Although minor upper GI symptoms, such as dyspepsia, are common and can occur anytime during therapy, physicians should remain alert for signs of ulceration and bleeding, even in the absence of previous GI symptoms. Physicians should inform patients about the signs and symptoms of GI side effects and what steps to take if they occur.

Risk Factors for GI Bleeding, Ulceration, and Perforation

Patients with a prior history of peptic ulcer disease and/or GI bleeding who used NSAIDs had a greater than 10-fold increased risk for developing a GI bleed compared to patients without these risk factors. Other factors that increase the risk for of GI bleeding in patients treated with NSAIDs include longer duration of NSAID therapy; concomitant use of oral corticosteroids, aspirin, anticoagulants, or selective serotonin reuptake inhibitors (SSRIs); smoking; use of alcohol; older age; and poor general health status. Most postmarketing reports of fatal GI events occurred in elderly or debilitated patients. Additionally, patients with advanced liver disease and/or coagulopathy are at increased risk for GI bleeding.

Strategies to Minimize the GI Risks in NSAID-treated patients

- Use the lowest effective dosage for the shortest possible duration.
- Avoid administration of more than one NSAID at a time.
- Avoid use in patients at higher risk unless benefits are expected to outweigh the increased risk of bleeding. For high risk such patients, as well as those with active GI bleeding, consider alternate therapies other than NSAIDs.
- Remain alert for signs and symptoms of GI ulceration and bleeding during NSAID therapy.
- If a serious GI adverse event is suspected, promptly initiate evaluation and treatment, and discontinue Hydrocodone Bitartrate and Aspirin Tablets until a serious GI adverse event is ruled out.
- In the setting of concomitant use of low-dose aspirin for cardiac prophylaxis, monitor patients more closely for evidence of GI bleeding [see DRUG INTERACTIONS].

Increased Risk of Seizures in Patients with Seizure Disorders

The hydrocodone in Hydrocodone Bitartrate and Aspirin Tablets may increase the frequency of seizures in patients with seizure disorders, and may increase the risk of seizures occurring in other clinical settings associated with seizures. Regularly evaluate patients with a history of seizure disorders for worsened seizure control during Hydrocodone Bitartrate and Aspirin Tablet therapy.

Withdrawal

Do not abruptly discontinue Hydrocodone Bitartrate and Aspirin Tablets in a patient physically dependent on opioids. When discontinuing Hydrocodone Bitartrate and Aspirin Tablets in a physically-dependent patient, gradually taper the dosage. Rapid tapering of hydrocodone in a patient physically dependent on opioids may lead to a withdrawal syndrome and return of pain [see DOSAGE AND ADMINISTRATION, DRUG ABUSE AND DEPENDENCE].

Additionally, avoid the use of mixed agonist/antagonist (e.g., pentazocine, nalbuphine, and butorphanol) or partial agonist (e.g., buprenorphine) analgesics in patients who are receiving a full opioid agonist analgesic, including Hydrocodone Bitartrate and Aspirin Tablets. In these patients, mixed agonist/antagonist and partial analgesics may reduce the analgesic effect and/or precipitate withdrawal symptoms [see PRECAUTIONS; Drug Interactions].

Fetal Toxicity

Premature Closure of Fetal Ductus Arteriosus:

Avoid use of NSAIDs, including Hydrocodone Bitartrate and Aspirin Tablets, in pregnant women at about 30 weeks gestation and later. NSAIDs including Hydrocodone Bitartrate and Aspirin Tablets, increase the risk of premature closure of the fetal ductus arteriosus at approximately this gestational age.

Oligohydramnios/Neonatal Renal Impairment:

Use of NSAIDs, including Hydrocodone Bitartrate and Aspirin Tablets, at about 20 weeks gestation or later in pregnancy may cause fetal renal dysfunction leading to oligohydramnios and, in some cases, neonatal renal impairment. These adverse outcomes are seen, on average, after days to weeks of treatment, although oligohydramnios has been infrequently reported as soon as 48 hours after NSAID initiation. Oligohydramnios is often, but not always, reversible with treatment discontinuation. Complications of prolonged oligohydramnios may, for example, include limb contractures and delayed lung maturation. In some postmarketing cases of impaired neonatal renal function, invasive procedures such as exchange transfusion or dialysis were required. If NSAID treatment is necessary between about 20 weeks and 30 weeks gestation, limit Hydrocodone Bitartrate and Aspirin Tablets use to the lowest effective dose and shortest duration possible. Consider ultrasound monitoring of amniotic fluid if Hydrocodone Bitartrate and Aspirin Tablets treatment extends beyond 48 hours. Discontinue Hydrocodone Bitartrate and Aspirin Tablets if oligohydramnios occurs and follow up according to clinical practice [see PRECAUTIONS; Pregnancy].

Risks of Driving and Operating Machinery

Hydrocodone Bitartrate and Aspirin Tablets may impair the mental or physical abilities needed to perform potentially hazardous activities such as driving a car or operating machinery. Warn patients not to drive or operate dangerous machinery unless they are tolerant to the effects of Hydrocodone Bitartrate and Aspirin Tablets and know how they will react to the medication [see PRECAUTIONS; Information for Patients/Caregivers].

Hypersensitivity to Hydrocodone of Aspirin, (e.g. angioedema)

Hydrocodone Bitartrate and Aspirin Tablets are contraindicated in patients with known hypersensitivity to hydrocodone or aspirin, and in any situation where opioids or aspirin are contraindicated. Aspirin is contraindicated in patients with known allergy to nonsteroidal anti-inflammatory drug products (NSAIDs) and in patients with the syndrome of asthma, rhinitis, and nasal polyps. Aspirin may cause severe urticaria, angioedema, or bronchospasm (asthma).

Coagulation Abnormalities and Bleeding Risks

Even low doses of aspirin can inhibit platelet function leading to an increase in bleeding time. This can adversely affect patients with inherited (hemophilia) or acquired (liver disease or vitamin K deficiency) bleeding disorders.

Aspirin is contraindicated in patients with hemophilia.

Aspirin administered pre-operatively may prolong bleeding time.

Alcohol Warning

Patients who consume three or more alcoholic drinks every day should be counseled about the bleeding risks involved with chronic, heavy alcohol use while taking aspirin.

Risk of Reye’s Syndrome When Used for Treatment of Viral Infections in Children or Teenagers

Aspirin should not be used in children or teenagers for viral infections, with or without fever, because of the risk of Reye’s syndrome with concomitant use of aspirin in certain viral illnesses.

Drug Rash with Eosinophilia and Systemic Symptoms (DRESS)

Drug Reaction with Eosinophilia and Systemic Symptoms (DRESS) has been reported in patients taking NSAIDs such as Hydrocodone Bitartrate and Aspirin Tablets. Some of these events have been fatal or life-threatening. DRESS typically, although not exclusively, presents with fever, rash, lymphadenopathy, and/or facial swelling. Other clinical manifestations may include hepatitis, nephritis, hematological abnormalities, myocarditis, or myositis. Sometimes symptoms of DRESS may resemble an acute viral infection. Eosinophilia is often present. Because this disorder is variable in its presentation, other organ systems not noted here may be involved. It is important to note that early manifestations of hypersensitivity, such as fever or lymphadenopathy, may be present even though rash is not evident. If such signs or symptoms are present, discontinue Hydrocodone Bitartrate and Aspirin Tablets and evaluate the patient immediately.

PRECAUTIONS

General

Aspirin has been associated with elevated hepatic enzymes, blood urea nitrogen and serum creatinine, hyperkalemia, proteinuria, and prolonged bleeding time.

Hemorrhage

Aspirin may increase the likelihood of hemorrhage due to its effect on the gastric mucosa and platelet function (prolongation of bleeding time). Salicylates should be used with caution in the presence of peptic ulcer or coagulation abnormalities.

Ambulatory Surgery and Postoperative Use

Hydrocodone and other morphine-like opioids have been shown to decrease bowel motility. Ileus is a common postoperative complication, especially after intra-abdominal surgery with use of opioid analgesia. Caution should be taken to monitor for decreased bowel motility in postoperative patients receiving opioids. Standard supportive therapy should be implemented.

Renal Toxicity and Hyperkalemia

Renal Toxicity

Long-term administration of NSAIDs has resulted in renal papillary necrosis and other renal injury.

Renal toxicity has also been seen in patients in whom renal prostaglandins have a compensatory role in the maintenance of renal perfusion. In these patients, administration of an NSAID may cause a dose-dependent reduction in prostaglandin formation and, secondarily, in renal blood flow, which may precipitate overt renal decompensation. Patients at greatest risk of this reaction are those with impaired renal function, dehydration, hypovolemia, heart failure, liver dysfunction, those taking diuretics and ACE inhibitors or ARBs, and the elderly. Discontinuation of NSAID therapy is usually followed by recovery to the pretreatment state.

No information is available from controlled clinical studies regarding the use of Hydrocodone Bitartrate and Aspirin Tablets in patients with advanced renal disease. The renal effects of Hydrocodone Bitartrate and Aspirin Tablets may hasten the progression of renal dysfunction in patients with pre-existing renal disease.

Correct volume status in dehydrated or hypovolemic patients prior to initiating Hydrocodone Bitartrate and Aspirin Tablets. Monitor renal function in patients with renal or hepatic impairment, heart failure, dehydration, or hypovolemia during use of Hydrocodone Bitartrate and Aspirin Tablets (see PRECAUTIONS; Drug Interactions]. Avoid the use of Hydrocodone Bitartrate and Aspirin Tablets in patients with advanced renal disease unless the benefits are expected to outweigh the risk of worsening renal function. If Hydrocodone Bitartrate and Aspirin Tablets is used in patients with advanced renal disease, monitor patients for signs of worsening renal function.

Hyperkalemia

Increases in serum potassium concentration, including hyperkalemia, have been reported with use of NSAIDs, even in some patients without renal impairment. In patients with normal renal function, these effects have been attributed to a hyporeninemic-hypoaldosteronism state.

Premature Closure of Fetal Ductus Arteriosus

Aspirin may cause premature closure of the fetal ductus arteriosus. Avoid use of NSAIDs, including Hydrocodone Bitartrate and Aspirin Tablets, in pregnant women starting at 30 weeks of gestation (third trimester) [see PRECAUTIONS].

Information for Patients/Caregivers

Advise the patient to read the FDA-approved patient labeling (Medication Guide).

Storage and Disposal

Because of the risks associated with accidental ingestion, misuse, and abuse, advise patients to store Hydrocodone Bitartrate and Aspirin Tablets securely, out of sight and reach of children, and in a location not accessible by others, including visitors to the home. Inform patients that leaving Hydrocodone Bitartrate and Aspirin Tablets unsecured can pose a deadly risk to others in the home [see WARNINGS, DRUG ABUSE AND DEPENDENCE].

Advise patients and caregivers that when medicines are no longer needed, they should be disposed of promptly. Expired, unwanted, or unused Hydrocodone Bitartrate and Aspirin Tablets should be disposed of by flushing the unused medication down the toilet if a drug take-back option is not readily available. Inform patients that they can visit www.fda.gov/drugdisposal for a complete list of medicines recommended for disposal by flushing, as well as additional information on disposal of unused medicines.

Addiction, Abuse, and Misuse

Inform patients that the use of Hydrocodone Bitartrate and Aspirin Tablets, even when taken as recommended, can result in addiction, abuse, and misuse, which can lead to overdose and death [see WARNINGS]. Instruct patients not to share Hydrocodone Bitartrate and Aspirin Tablets with others and to take steps to protect Hydrocodone Bitartrate and Aspirin Tablets from theft or misuse.

Life-Threatening Respiratory Depression

Inform patients of the risk of life-threatening respiratory depression, including information that the risk is greatest when starting Hydrocodone Bitartrate and Aspirin Tablets or when the dosage is increased, and that it can occur even at recommended dosages [see WARNINGS]. Advise patients how to recognize respiratory depression and to seek medical attention if breathing difficulties develop.

Educate patients and caregivers on how to recognize respiratory depression and emphasize the importance of calling 911 or getting emergency medical help right away in the event of a known or suspected overdose.

Accidental Ingestion

Inform patients that accidental ingestion, especially by children, may result in respiratory depression or death [see WARNINGS]. Instruct patients to take steps to store Hydrocodone Bitartrate and Aspirin Tablets securely and to dispose of unused Hydrocodone Bitartrate and Aspirin Tablets by flushing down the toilet.

Interactions with Benzodiazepines and Other CNS Depressants

Inform patients and caregivers that potentially fatal additive effects may occur if Hydrocodone Bitartrate and Aspirin Tablets are used with benzodiazepine and/or other CNS depressants, including alcohol, and not to use these concomitantly unless supervised by a healthcare provider [see WARNINGS, PRECAUTIONS; Drug Interactions].

Patient Access to Naloxone for the Emergency Treatment of Opioid Overdose

Discuss with the patient and caregiver the availability of naloxone for the emergency treatment of opioid overdose, both when initiating and renewing treatment with Hydrocodone Bitartrate and Aspirin Tablets. Inform patients and caregivers about the various ways to obtain naloxone as permitted by individual state naloxone dispensing and prescribing regulations (e.g., by prescription, directly from a pharmacist, or as part of a community-based program) [see WARNINGS; Life-Threatening Respiratory Depression, DOSAGE AND ADMINISTRATION; Initial Dosage].

Educate patients and caregivers on how to recognize the signs and symptoms of an overdose.

Explain to patients and caregivers that naloxone’s effects are temporary, and that they must call 911 or get emergency medical help right away in all cases of known or suspected opioid overdose, even if naloxone is administered [see OVERDOSAGE].

If naloxone is prescribed, also advise patients and caregivers:

- How to treat with naloxone in the event of an opioid overdose
- To tell family and friends about their naloxone and to keep it in a place where family and friends can access it in an emergency
- To read the Patient Information (or other educational material) that will come with their naloxone Emphasize the importance of doing this before an opioid emergency happens, so the patient and caregiver will know what to do.

Hyperalgesia and Allodynia

Inform patients and caregivers not to increase opioid dosage without first consulting a clinician. Advise patients to seek medical attention if they experience symptoms of hyperalgesia, including worsening pain, increased sensitivity to pain, or new pain [see Warnings, Adverse Reactions].

Serotonin Syndrome

Inform patients that opioids could cause a rare but potentially life-threatening condition resulting from concomitant administration of serotonergic drugs. Warn patients of the symptoms of serotonin syndrome and to seek medical attention right away if symptoms develop. Instruct patients to inform their healthcare providers if they are taking, or plan to take serotonergic medications [see PRECAUTIONS; Drug Interactions].

Monoamine Oxidase Inhibitor (MAOI) Interaction

Inform patients to avoid taking Hydrocodone Bitartrate and Aspirin Tablets while using any drugs that inhibit monoamine oxidase. Patients should not start MAOIs while taking Hydrocodone Bitartrate and Aspirin Tablets [see PRECAUTIONS; Drug Interactions].

Important Administration Instructions

Instruct patients how to properly take Hydrocodone Bitartrate and Aspirin Tablets. The usual dosage is one or two tablets every four to six hours as needed for pain. The maximum daily dose of aspirin should not exceed 4 grams [see DOSAGE AND ADMINISTRATION, PRECAUTIONS].

Important Discontinuation Instructions

In order to avoid developing withdrawal symptoms, instruct patients not to discontinue Hydrocodone Bitartrate and Aspirin Tablets without first discussing a tapering plan with the prescriber [see DOSAGE AND ADMINISTRATION].

Driving or Operating Heavy Machinery

Inform patients that Hydrocodone Bitartrate and Aspirin Tablets may impair the ability to perform potentially hazardous activities such as driving a car or operating heavy machinery. Advise patients not to perform such tasks until they know how they will react to the medication [see WARNINGS].

Constipation

Advise patients of the potential for severe constipation, including management instructions and when to seek medical attention [see ADVERSE REACTIONS, CLINICAL PHARMACOLOGY].

Adrenal Insufficiency

Inform patients that the opioids could cause adrenal insufficiency, a potentially life-threatening condition. Adrenal insufficiency may present with non-specific symptoms and signs such as nausea, vomiting, anorexia, fatigue, weakness, dizziness, and low blood pressure. Advise patients to seek medical attention if they experience a constellation of these symptoms [see WARNINGS].

Hypotension

Inform patients that Hydrocodone Bitartrate and Aspirin Tablets may cause orthostatic hypotension and syncope. Instruct patients how to recognize symptoms of low blood pressure and how to reduce the risk of serious consequences should hypotension occur (e.g., sit or lie down, carefully rise from a sitting or lying position) [see WARNINGS].

Anaphylaxis

Inform patients that anaphylaxis has been reported with ingredients contained in Hydrocodone Bitartrate and Aspirin Tablets. Advise patients how to recognize such a reaction and when to seek medical attention [see CONTRAINDICATIONS, ADVERSE REACTIONS].

Serious Skin Reactions, including DRESS

Advise patients to stop taking Hydrocodone Bitartrate and Aspirin Tablets immediately if they develop any type of rash or fever and to contact their healthcare provider as soon as possible [see WARNINGS].

Aspirin Allergy

Patients should be informed that Hydrocodone Bitartrate and Aspirin Tablets contain aspirin and should not be taken by patients with an aspirin or NSAID allergy.

Pregnancy

Neonatal Opioid Withdrawal Syndrome

Inform female patients of reproductive potential that the use of Hydrocodone Bitartrate and Aspirin Tablets for an extended period of time during pregnancy can result in neonatal opioid withdrawal syndrome, which may be life-threatening if not recognized and treated [see WARNINGS, PRECAUTIONS; Pregnancy].

Embryo-Fetal Toxicity

Inform female patients of reproductive potential that Hydrocodone Bitartrate and Aspirin Tablets can cause fetal harm and to inform their healthcare provider of a known or suspected pregnancy. Avoid use of Hydrocodone Bitartrate and Aspirin Tablets and other NSAIDs starting at 30 weeks gestation because of the risk of the premature closing of the fetal ductus arteriosus [see WARNINGS; Premature Closure of the Ductus Arteriosus, PRECAUTIONS; Pregnancy].

Inform pregnant women to avoid use of aspirin and other NSAIDs starting at 30 weeks gestation because of the risk of the premature closing of the fetal ductus arteriosus. If treatment with Hydrocodone Bitartrate and Aspirin Tablets is needed for a pregnant woman between about 20 to 30 weeks gestation, advise her that she may need to be monitored for oligohydramnios, if treatment continues for longer than 48 hours [see WARNINGS; Fetal Toxicity, PRECAUTIONS; Pregnancy].

Lactation

Advise nursing mothers to carefully observe infants for increased sleepiness (more than usual), breathing difficulties, or limpness. Instruct nursing mothers to seek immediate medical care if they notice these signs [see PRECAUTIONS; Nursing Mothers (Lactation)].

Infertility

Inform patients that use of opioids for extended period of time may cause reduced fertility. It is not known whether these effects on fertility are reversible [see ADVERSE REACTIONS]. Advise females of reproductive potential who desire pregnancy that NSAIDs, including Hydrocodone Bitartrate and Aspirin Tablets, may be associated with a reversible delay in ovulation [see Use in Specific Populations (PRECAUTIONS; Carcinogenesis, Mutagenesis, Impairment of Fertility)].

Risk of Bleeding

Inform patients about the signs and symptoms of bleeding. Tell patients to notify their physician if they are prescribed any drug which may increase risk of bleeding.

Counsel patients who consume three or more alcoholic drinks daily about the bleeding risks involved with chronic, heavy alcohol use while taking aspirin [see WARNINGS].

Avoid Concomitant Use of NSAIDs

Inform patients that the concomitant use of Hydrocodone Bitartrate and Aspirin Tablets with NSAIDs or other salicylates (e.g., diflunisal, salsalate) is not recommended due to the increased risk of gastrointestinal toxicity, and little or no increase in efficacy [see WARNINGS, PRECAUTIONS; Drug Interactions]. Alert patients that NSAIDs may be present in "over the counter" medications for treatment of colds, fever, or insomnia.

Laboratory Tests

Aspirin has been associated with elevated hepatic enzymes, blood urea nitrogen and serum creatinine, hyperkalemia, proteinuria, and prolonged bleeding time. In patients with severe hepatic or renal disease, effects of therapy should be followed with serial liver and/or renal function tests.

Hypersensitivity to aspirin cannot be detected by skin testing or radioimmunoassay procedure.

Drug Interactions

Table 1: Clinically Significant Drug Interactions with Hydrocodone Bitartrate and Aspirin Tablets
Inhibitors of CYP3A4 and CYP2D6
Clinical Impact: | The concomitant use of Hydrocodone Bitartrate and Aspirin Tablets and CYP3A4 inhibitors can increase the plasma concentration of hydrocodone, resulting in increased or prolonged opioid effects. These effects could be more pronounced with concomitant use of Hydrocodone Bitartrate and Aspirin Tablets and CYP2D6 and CYP3A4 inhibitors, particularly when an inhibitor is added after a stable dose of Hydrocodone Bitartrate and Aspirin Tablets is achieved [see WARNINGS]. After stopping CYP3A4 inhibitor, as the effects of the inhibitor decline, the hydrocodone plasma concentration will decrease [see CLINICAL PHARMACOLOGY], resulting in decreased opioid efficacy or a withdrawal syndrome in patients who had developed physical dependence to hydrocodone.
Intervention: | If concomitant use is necessary, consider dosage reduction of Hydrocodone Bitartrate and Aspirin Tablets until stable drug effects are achieved. Evaluate patients at frequent intervals for respiratory depression and sedation. If a CYP3A4 inhibitor is discontinued, consider increasing the Hydrocodone Bitartrate and Aspirin Tablets dosage until stable drug effects are achieved. Evaluate for signs of opioid withdrawal.
Examples: | Macrolide antibiotics (e.g., erythromycin), azole-antifungal agents (e.g. ketoconazole), protease inhibitors (e.g., ritonavir)
CYP3A4 Inducers
Clinical Impact: | The concomitant use of Hydrocodone Bitartrate and Aspirin Tablets and CYP3A4 inducers can decrease the plasma concentration of hydrocodone [see CLINICAL PHARMACOLOGY], resulting in decreased efficacy or onset of a withdrawal syndrome in patients who have developed physical dependence to hydrocodone [see WARNINGS]. After stopping a CYP3A4 inducer, as the effects of the inducer decline, the hydrocodone plasma concentration will increase [see CLINICAL PHARMACOLOGY], which could increase or prolong both the therapeutic effects and adverse reactions, and may cause serious respiratory depression.
Intervention: | If concomitant use is necessary, consider increasing the Hydrocodone Bitartrate and Aspirin Tablets dosage until stable drug effects are achieved. Evaluate for signs of opioid withdrawal. If a CYP3A4 inducer is discontinued, consider Hydrocodone Bitartrate and Aspirin Tablets dosage reduction and evaluate patients at frequent intervals for signs of respiratory depression and sedation.
Examples: | Rifampin, carbamazepine, phenytoin
Benzodiazepines and other Central Nervous System (CNS) Depressants
Clinical Impact: | Due to additive pharmacologic effect, the concomitant use of benzodiazepines or other CNS depressants including alcohol, increases the risk of respiratory depression, profound sedation, coma, and death.
Intervention: | Reserve concomitant prescribing of these drugs for use in patients for whom alternative treatment options are inadequate. Limit dosages and durations to the minimum required. Inform patients and caregivers of this potential interaction, educate them on the signs and symptoms of respiratory depression (including sedation). If concomitant use is warranted, consider prescribing naloxone for the emergency treatment of opioid overdose [see WARNINGS].
Examples: | Benzodiazepines and other sedatives/hypnotics, anxiolytics, tranquilizers, muscle relaxants, general anesthetics, antipsychotics, other opioids, alcohol.
Serotonergic Drugs
Clinical Impact: | The concomitant use of opioids with other drugs that affect the serotonergic neurotransmitter system has resulted in serotonin syndrome.
Intervention: | If concomitant use is warranted, frequently evaluate the patient, particularly during treatment initiation and dose adjustment. Discontinue Hydrocodone Bitartrate and Aspirin Tablets if serotonin syndrome is suspected.
Examples: | Selective serotonin reuptake inhibitors (SSRIs), serotonin and norepinephrine reuptake inhibitors (SNRIs), tricyclic antidepressants (TCAs), triptans, 5-HT3 receptor antagonists, drugs that effect the serotonin neurotransmitter system (e.g., mirtazapine, trazodone, tramadol), certain muscle relaxants (i.e., cyclobenzaprine, metaxalone), monoamine oxidase (MAO) inhibitors (those intended to treat psychiatric disorders and also others, such as linezolid and intravenous methylene blue).
Monoamine Oxidase Inhibitors (MAOIs)
Clinical Impact: | MAOI interactions with opioids may manifest as serotonin syndrome or opioid toxicity (e.g., respiratory depression, coma) [see WARNINGS].
Intervention: | The use of Hydrocodone Bitartrate and Aspirin Tablets is not recommended for patients taking MAOIs or within 14 days of stopping such treatment. If urgent use of an opioid is necessary, use test doses and frequent titration of small doses to treat pain while closely evaluating blood pressure and signs and symptoms of CNS and respiratory depression.
Examples: | Phenelzine, tranylcypromine, linezolid
Mixed Agonist/Antagonist and Partial Agonist Opioid Analgesics
Clinical Impact: | May reduce the analgesic effect of Hydrocodone Bitartrate and Aspirin Tablets and/or precipitate withdrawal symptoms
Intervention: | Avoid concomitant use.
Examples: | Butorphanol, nalbuphine, pentazocine, buprenorphine
Muscle Relaxants
Clinical Impact: | Hydrocodone may enhance the neuromuscular blocking action of skeletal muscle relaxants and produce an increased degree of respiratory depression.
Intervention: | Because respiratory depression may be greater than otherwise expected, decrease the dosage of Hydrocodone Bitartrate and Aspirin Tablets and/or the muscle relaxant as necessary. Due to the risk of respiratory depression with concomitant use of muscle relaxants and opioids, consider prescribing naloxone for the emergency treatment of opioid overdose.
Diuretics
Clinical Impact: | Opioids can reduce the efficacy of diuretics by inducing the release of antidiuretic hormone. The effectiveness of diuretics in patients with underlying renal or cardiovascular disease may be diminished by the concomitant administration of aspirin due to inhibition of renal prostaglandins, leading to decreased renal blood flow and salt and fluid retention.
Intervention: | Evaluate patients for signs of diminished diuresis and/or effects on blood pressure and increase the dosage of the diuretic as needed.
Anticholinergic Drugs
Clinical Impact: | The concomitant use of anticholinergic drugs may increase risk of urinary retention and/or severe constipation, which may lead to paralytic ileus.
Intervention: | Evaluate patients for signs of urinary retention or reduced gastric motility when Hydrocodone Bitartrate and Aspirin Tablets is used concomitantly with anticholinergic drugs.
Anticoagulants
Clinical Impact: | Aspirin may enhance the effects of anticoagulants. Concurrent use may increase the risk of bleeding. Aspirin can also displace warfarin from protein binding sites, leading to prolongation of both the prothrombin time and the bleeding time.
Intervention: | Follow patients for signs of bleeding.
Examples: | Warfarin, heparin, enoxaparin, clopidogrel, prasugrel, rivaroxaban, apixaban
Uricosuric Agents
Clinical Impact: | Aspirin inhibits the uricosuric effects of uricosuric agents.
Intervention: | Avoid concomitant use.
Examples: | Probenecid
Carbonic Anhydrase Inhibitors
Clinical Impact: | Concurrent use with aspirin can lead to high serum concentrations of the carbonic anhydrase inhibitor and cause toxicity due to competition at the renal tubule for secretion.
Intervention: | Consider reducing the dose of the carbonic anhydrase inhibitor and follow patient for any adverse effects from the carbonic anhydrase inhibitor.
Examples: | Acetazolamide, methazolamide
Methotrexate
Clinical Impact: | Aspirin may enhance the toxicity of methotrexate by displacing it from its plasma protein binding sites and/or reducing its renal clearance.
Intervention: | Use caution if using concomitantly, especially in elderly patients or patients with renal impairment. Follow patients for methotrexate toxicity.
Nephrotoxic Agents
Clinical Impact: | Concomitant use with aspirin may lead to additive nephrotoxicity due to the inhibition of renal prostaglandins by aspirin. Also, the plasma concentration of aspirin is increased by conditions that reduce the glomerular filtration rate or tubular secretion.
Intervention: | Use Hydrocodone Bitartrate and Aspirin Tablets with caution if used concomitantly with nephrotoxic agents. Closely follow the renal function of patients.
Examples: | Aminoglycosides, amphotericin B, systemic bacitracin, cisplatin, cyclosporine, foscarnet, or parenteral vancomycin
Angiotensin Converting Enzyme (ACE) Inhibitors
Clinical Impact: | The hyponatremic and hypotensive effects of ACE inhibitors may be diminished by the concomitant administration of aspirin due to its indirect effect on the renin-angiotensin conversion pathway.
Intervention: | Use caution if using concomitantly. Follow the blood pressure and renal function of patients.
Examples: | Ramipril, captopril
Beta Blockers
Clinical Impact: | The hypotensive effects of beta blockers may be diminished by the concomitant administration of aspirin due to inhibition of renal prostaglandins, leading to decreased renal blood flow, and salt and fluid retention.
Intervention: | Use caution if using concomitantly. Follow the blood pressure and renal function of patients.
Examples: | Metoprolol, propranolol
Hypoglycemic Agents
Clinical Impact: | Aspirin may increase the serum glucose-lowering action of insulin and sulfonylureas leading to hypoglycemia.
Intervention: | Patients should be advised to consult a physician if any signs or symptoms of hypoglycemia occur.
Examples: | Insulin, glimepiride, glipizide
Anticonvulsants
Clinical Impact: | Aspirin can displace protein-bound phenytoin and valproic acid, leading to a decrease in the total concentration of phenytoin and an increase in serum valproic acid levels.
Intervention: | Use caution if using concomitantly.
Examples: | Phenytoin, valproic acid
Nonsteroidal Anti-inflammatory Drugs (NSAIDs)
Clinical Impact: | Concurrent use of aspirin with other NSAIDs may increase the risk of bleeding or lead to decreased renal function. Aspirin may enhance serious side effects and toxicity of ketorolac by displacing it from its plasma protein binding sites and/or reducing its renal clearance.
Intervention: | Avoid concomitant use.
Examples: | Ketoralac, ibuprofen, naproxen, diclofenac
Corticosteroids
Clinical Impact: | In patients receiving concomitant corticosteroids and chronic use of aspirin, withdrawal of corticosteroids may result in salicylism because corticosteroids enhance renal clearance of salicylates and their withdrawal is followed by return to normal rates of renal clearance.
Intervention: | Avoid concomitant use.

Drug/Laboratory Test Interactions

Depending on the sensitivity/specificity and the test methodology, the individual components of Hydrocodone Bitartrate and Aspirin Tablets may cross-react with assays used in the preliminary detection of cocaine (primary urinary metabolite, benzoylecgonine) or marijuana (cannabinoids) in human urine. A more specific alternate chemical method must be used in order to obtain a confirmed analytical result. The preferred confirmatory method is gas chromatography/mass spectrometry (GC/MS). Moreover, clinical considerations and professional judgment should be applied to any drug-of-abuse test result, particularly when preliminary positive results are used.

Salicylates may increase the protein bound iodine (PBI) result by competing for the protein binding sites on pre-albumin and possibly thyroid-binding globulins.

Aspirin

Aspirin may interfere with the following laboratory determinations:

In blood: serum amylase, fasting blood glucose, carbon dioxide, cholesterol, protein, protein bound iodine, uric acid, prothrombin time, bleeding time, and spectrophotometric detection of barbiturates.

In urine: glucose, 5-hydroxyindoleacetic acid, Gerhardt ketone, vanillylmandelic acid (VMA), protein, uric acid, and diacetic acid.

Carcinogenesis, Mutagenesis, Impairment of Fertility

Carcinogenesis

Long-term studies to evaluate the carcinogenic potential of the combination of Hydrocodone Bitartrate and Aspirin Tablets have not been conducted.

Administration of aspirin for 68 weeks at 0.5 percent in the feed of rats was not carcinogenic.

Mutagenesis

The combination of hydrocodone and aspirin has not been evaluated for mutagenicity.

In the Ames Salmonella assay, aspirin was not mutagenic; however, aspirin did induce chromosome aberrations in cultured human fibroblasts.

Impairment of Fertility

Animal studies to evaluate the effects of hydrocodone on fertility have not been conducted. Aspirin has been shown to inhibit ovulation in rats.

Pregnancy

Risk Summary

Use of NSAIDs, including aspirin, can cause premature closure of the fetal ductus arteriosus and fetal renal dysfunction leading to oligohydramnios and, in some cases, neonatal renal impairment. Because of these risks, limit dose and duration of Hydrocodone Bitartrate and Aspirin Tablets use between about 20 weeks of gestation, and avoid Hydrocodone Bitartrate and Aspirin Tablets use at about 30 weeks of gestation and later in pregnancy [see WARNINGS; Fetal Toxicity].

Premature Closure of Fetal Ductus Arteriosus

Use of NSAIDs, including aspirin, at about 30 weeks gestation or later in pregnancy increases the risk of premature closure of the fetal ductus arteriosus.

Oligohydramnios/Neonatal Renal Impairment

Use of NSAIDs at about 20 weeks gestation or later in pregnancy has been associated with cases of fetal renal dysfunction leading to oligohydramnios, and in some cases, neonatal renal impairment.

Data from observational studies regarding other potential embryofetal risks of NSAID use in women in the first or second trimesters of pregnancy are inconclusive.

Based on animal data, prostaglandins have been shown to have an important role in endometrial vascular permeability, blastocyst implantation, and decidualization. In animal studies, administration of prostaglandin synthesis inhibitors such as aspirin, resulted in increased pre- and post-implantation loss. Prostaglandins also have been shown to have an important role in fetal kidney development. In published animal studies, prostaglandin synthesis inhibitors have been reported to impair kidney development when administered at clinically relevant doses.

The estimated background risk of major birth defects and miscarriage for the indicated population(s) is unknown. All pregnancies have a background risk of birth defect, loss, or other adverse outcomes. In the U.S. general population, the estimated background risk of major birth defects and miscarriage in clinically recognized pregnancies is 2% to 4% and 15% to 20% respectively.

Clinical Considerations

Fetal/Neonatal Adverse Reactions

Use of opioid analgesics for an extended period of time during pregnancy for medical or nonmedical purposes can result in physical dependence in the neonate and neonatal opioid withdrawal syndrome shortly after birth.

Neonatal opioid withdrawal syndrome presents as irritability, hyperactivity, abnormal sleep pattern, high pitched cry, tremor, vomiting, diarrhea and failure to gain weight. The onset, duration, and severity of neonatal opioid withdrawal syndrome vary based on the specific opioid used, duration of use, timing and amount of last maternal use, and rate of elimination of the drug by the newborn. Observe newborns for symptoms of neonatal opioid withdrawal syndrome and manage accordingly [see WARNINGS].

Premature Closure of Fetal Ductus Arteriosus:

Avoid use of NSAIDs in women at about 30 weeks gestation and later in pregnancy, because NSAIDs, including Hydrocodone Bitartrate and Aspirin Tablets, can cause premature closure of the fetal ductus arteriosus [see WARNINGS; Fetal Toxicity].

Oligohydramnios/Neonatal Renal Impairment

If an NSAID is necessary at about 20 weeks gestation or later in pregnancy, limit the use to the lowest effective dose and shortest duration possible. If Hydrocodone Bitartrate and Aspirin Tablets treatment extends beyond 48 hours, consider monitoring with ultrasound for oligohydramnios. If oligohydramnios occurs, discontinue Hydrocodone Bitartrate and Aspirin Tablets and follow up according to clinical practice [see WARNINGS; Fetal Toxicity].

Labor and Delivery

Opioids cross the placenta and may produce respiratory depression and psycho-physiologic effects in neonates. An opioid antagonist, such as naloxone must be available for reversal of opioid-induced respiratory depression in the neonate. Hydrocodone Bitartrate and Aspirin Tablets is not recommended for use in women during and immediately prior to labor, when use of shorter acting analgesics or other analgesic techniques are more appropriate. Occasionally, opioid analgesics, including Hydrocodone Bitartrate and Aspirin Tablets, can prolong labor through actions which temporarily reduce the strength, duration, and frequency of uterine contractions. However this effect is not consistent and may be offset by an increased rate of cervical dilation, which tends to shorten labor. Monitor neonates exposed to opioid analgesics during labor for signs of excess sedation and respiratory depression.

Aspirin should be avoided one week prior to and during labor and delivery because it can result in excessive blood loss at delivery. Prolonged gestation and prolonged labor due to prostaglandin inhibition have been reported.

Data

Human Data

Premature Closure of Fetal Ductus Arteriosus:

Published literature reports that the use of NSAIDs at about 30 weeks of gestation and later in pregnancy may cause premature closure of the fetal ductus arteriosus.

Oligohydramnios/Neonatal Renal Impairment:

Published studies and postmarketing reports describe maternal NSAID use at about 20 weeks gestation or later in pregnancy associated with fetal renal dysfunction leading to oligohydramnios, and in some cases, neonatal renal impairment. These adverse outcomes are seen, on average, after days to weeks of treatment, although oligohydramnios has been infrequently as soon as 48 hours after NSAID initiation. In many cases, but not all, the decrease in amniotic fluid was transient and reversible with cessation of the drug. There have been a limited number of case reports of maternal NSAID use and neonatal renal dysfunction without oligohydramnios, some which were irreversible. Some cases of neonatal renal dysfunction required treatment with invasive procedures, such as exchange transfusion or dialysis.

Methodological limitations of these postmarketing studies and reports include lack of a control group; limited information regarding dose, duration, and timing of drug exposure; and concomitant use of other medications. These limitations preclude establishing a reliable estimate of the risk of adverse fetal and neonatal outcomes with maternal NSAID use. Because the published safety data on neonatal outcomes involved mostly preterm infants, the generalizability of certain reported risks to the full-term infant exposed to NSAIDs through maternal use is uncertain.

Animal Data

Animal reproduction studies with the combination of hydrocodone and aspirin or the individual drugs alone are not available.

Lactation

Risk Summary

Hydrocodone is present in human milk.

Salicylic acid has been detected in breast milk. Adverse effects on platelet function in the nursing infant exposed to aspirin in breast milk may be a potential risk. Furthermore, the risk of Reye’s Syndrome caused by salicylate in breast milk is unknown.

The developmental and health benefits of breastfeeding should be considered along with the mother's clinical need for Hydrocodone Bitartrate and Aspirin Tablets and any potential adverse effects on the breastfed infant from Hydrocodone Bitartrate and Aspirin Tablets or from the underlying maternal condition.

Clinical Considerations

Monitor infants exposed to Hydrocodone Bitartrate and Aspirin Tablets through breast milk for excess sedation and respiratory depression. Withdrawal symptoms can occur in breastfed infants when maternal administration of an opioid analgesic is stopped, or when breastfeeding is stopped.

Females and Males of Reproductive Potential

Infertility

Use of opioids for extended period of time may cause reduced fertility in females and males of reproductive potential. It is not known whether these effects on fertility are reversible [see ADVERSE REACTIONS].

Females

Based on the mechanism of action, the use of prostaglandin-mediated NSAIDs, including aspirin, may delay or prevent rupture of ovarian follicles, which has been associated with reversible infertility in some women. Published animal studies have shown that administration of prostaglandin synthesis inhibitors has the potential to disrupt prostaglandin-mediated follicular rupture required for ovulation. Small studies in women treated with NSAIDs have also shown a reversible delay in ovulation. Consider withdrawal of NSAIDs, including aspirin, in women who have difficulties conceiving or who are undergoing investigation of infertility.

Pediatric Use

Hydrocodone Bitartrate and Aspirin Tablets should not be administered to pediatric patients. Reye’s Syndrome is a rare but serious disease which can follow flu or chicken pox in children and teenagers. While the cause of Reye’s Syndrome is unknown, some reports claim aspirin (or salicylates) may increase the risk of developing this disease.

Geriatric Use

Elderly patients (aged 65 years or older) may have increased sensitivity to Hydrocodone Bitartrate and Aspirin Tablets. In general, use caution when selecting a dosage for an elderly patient, usually starting at the low end of the dosing range, reflecting the greater frequency of decreased hepatic, renal, or cardiac function and of concomitant disease or other drug therapy.

Respiratory depression is the chief risk for elderly patients treated with opioids, and has occurred after large initial doses were administered to patients who were not opioid-tolerant or when opioids were co-administered with other agents that depress respiration. Titrate the dosage of Hydrocodone Bitartrate and Aspirin Tablets slowly in geriatric patients and frequently reevaluate the patient for signs of central nervous system and respiratory depression [see WARNINGS].

Hydrocodone and aspirin are known to be substantially excreted by the kidney, and the risk of adverse reactions to this drug may be greater in patients with impaired renal function. Because elderly patients are more likely to have decreased renal function, care should be taken in dose selection, and it may be useful to regularly evaluate renal function.

Elderly patients, compared to younger patients, are at greater risk for NSAID-associated serious cardiovascular, gastrointestinal, and/or renal adverse reactions. If the anticipated benefit for the elderly patient outweighs these potential risks, dose selection should start at the low end of the dosing range, and follow patients for adverse effects [see WARNINGS, PRECAUTIONS].

Hepatic Impairment

Patients with hepatic impairment may have higher plasma hydrocodone concentrations than those with normal function. Use a low initial dose of Hydrocodone Bitartrate and Aspirin Tablets in patients with hepatic impairment and follow closely for adverse events such as respiratory depression and sedation.

Avoid aspirin in patients with severe hepatic impairment.

Renal Impairment

Patients with renal impairment may have higher plasma hydrocodone concentrations than those with normal function. Use a low initial dose Hydrocodone Bitartrate and Aspirin Tablets in patients with renal impairment and follow closely for adverse events such as respiratory depression and sedation.

Avoid aspirin in patients with severe renal impairment (glomerular filtration rate less than 10 mL/minute).

ADVERSE REACTIONS

The following serious adverse reactions are described, or described in greater detail, in other sections:

- Addiction, Abuse, and Misuse [see WARNINGS]
- Life-Threatening Respiratory Depression [see WARNINGS]
- Interactions with Benzodiazepines and Other CNS Depressants [see WARNINGS]
- Neonatal Opioid Withdrawal Syndrome [see WARNINGS]
- Opioid-Induced Hyperalgesia and Allodynia [see WARNINGS]
- Adrenal Insufficiency [see WARNINGS]
- Severe Hypotension [see WARNINGS]
- Gastrointestinal Adverse Reactions [see WARNINGS]
- Seizures [see WARNINGS]
- Withdrawal [see WARNINGS]
- Coagulation Abnormalities and Bleeding [see WARNINGS]
- Reye’s Syndrome [see WARNINGS]
- Renal Toxicity and Hyperkalemia [see PRECAUTIONS]
- Premature Closure of the Fetal Ductus Arteriosus [see PRECAUTIONS]

Postmarketing Experience

The following adverse reactions associated with the use of Hydrocodone Bitartrate and Aspirin Tablets were identified in clinical studies or postmarketing reports. Because some of these reactions were reported voluntarily from a population of uncertain size, it is not always possible to reliably estimate their frequency or establish a causal relationship to drug exposure.

Many adverse reactions due to aspirin ingestion are dose-related. The following is a list of adverse reactions that have been reported in the literature [see WARNINGS].

Body as a Whole: Fever, hypothermia, thirst.

Cardiovascular: Dysrhythmias, hypotension, tachycardia.

Central Nervous System: Agitation, cerebral edema, coma, confusion, dizziness, headache, subdural or intracranial hemorrhage, lethargy, seizures.

Fluid and Electrolyte: Dehydration, hyperkalemia, metabolic acidosis, respiratory alkalosis.

Gastrointestinal: Dyspepsia, GI bleeding, ulceration and perforation, nausea, vomiting, transient elevations of hepatic enzymes, hepatitis, Reye's Syndrome, pancreatitis.

Hematologic: Prolongation of the prothrombin time, disseminated intravascular coagulation, coagulopathy, thrombocytopenia.

Hypersensitivity: Acute anaphylaxis, angioedema, asthma, bronchospasm, laryngeal edema, urticaria.

Musculoskeletal: Rhabdomyolysis.

Metabolism: Hypoglycemia (in children), hyperglycemia.

Reproductive: Prolonged pregnancy and labor, stillbirths, lower birth weight infants, antepartum and postpartum bleeding.

Respiratory: Hyperpnea, pulmonary edema, tachypnea.

Special Senses: Hearing loss, tinnitus. Patients with high frequency hearing loss may have difficulty perceiving tinnitus. In these patients, tinnitus cannot be used as a clinical indicator of salicylism.

Urogenital: Interstitial nephritis, papillary necrosis, proteinuria, renal insufficiency and failure.

Serotonin syndrome: Cases of serotonin syndrome, a potentially life-threatening condition, have been reported during concomitant use of opioids with serotonergic drugs.

Adrenal insufficiency: Cases of adrenal insufficiency have been reported with opioid use, more often following greater than one month of use.

Anaphylaxis: Anaphylaxis has been reported with ingredients contained in Hydrocodone Bitartrate and Aspirin Tablets.

Androgen deficiency: Cases of androgen deficiency have with use of opioids for an extended period of time [see CLINICAL PHARMACOLOGY].

Hyperalgesia and Allodynia: Cases of hyperalgesia and allodynia have been reported with opioid therapy of any duration [see WARNINGS].

Hypoglycemia: Cases of hypoglycemia have been reported in patients taking opioids. Most reports were in patients with at least one predisposing risk factor (e.g., diabetes).

To report SUSPECTED ADVERSE REACTIONS, contact LGM Pharma Solutions, LLC at 1-877-288-1495 or FDA at 1-800-FDA-1088 or www.fda.gov/medwatch.

DRUG ABUSE AND DEPENDENCE

Controlled Substance

Hydrocodone Bitartrate and Aspirin Tablets contain hydrocodone, a Schedule II controlled substance.

Abuse

Hydrocodone Bitartrate and Aspirin Tablets contain hydrocodone, a substance with a high potential for misuse and abuse, which can lead to the development of substance use disorder, including addiction [see WARNINGS].

Misuse is the intentional use, for therapeutic purposes, of a drug by an individual in a way other than prescribed by a health care provider or for whom it was not prescribed.

Abuse is the intentional, non-therapeutic use of a drug, even once, for its desirable psychological or physiological effects.

Drug addiction is a cluster of behavioral, cognitive, and physiological phenomena that may include a strong desire to take the drug, difficulties in controlling drug use (e.g., continuing drug use despite harmful consequences, giving a higher priority to drug use than other activities and obligations), and possible tolerance or physical dependence.

Misuse and abuse of Hydrocodone Bitartrate and Aspirin Tablets increases risk of overdose, which may lead to central nervous system and respiratory depression, hypotension, seizures, and death. The risk is increased with concurrent abuse of Hydrocodone Bitartrate and Aspirin Tablets with alcohol and other CNS depressants. Abuse of and addiction to opioids in some individuals may not be accompanied by concurrent tolerance and symptoms of physical dependence. In addition, abuse of opioids can occur in the absence of addiction.

All patients treated with opioids require careful and frequent reevaluation for signs of misuse, abuse, and addiction, because use of opioid analgesic products carries the risk of addition even under appropriate medical use. Patients at high risk of Hydrocodone Bitartrate and Aspirin Tablets abuse include those with a history of prolonged use of any opioid, including products containing hydrocodone, those with a history of drug or alcohol abuse, or those who use Hydrocodone Bitartrate and Aspirin Tablets in combination with other abused drugs.

“Drug-seeking” behavior is very common in persons with substance use disorders. Drug-seeking tactics include emergency calls or visits near the end of office hours, refusal to undergo appropriate examination, testing, or referral, repeated "loss" of prescriptions, tampering with prescriptions, and reluctance to provide prior medical records or contact information for other treating healthcare provider(s). “Doctor shopping” (visiting multiple prescribers to obtain additional prescriptions) is common among people who abuse drugs and people with substance use disorder. Preoccupation with achieving adequate pain relief can be appropriate behavior in a patient with inadequate pain control.

Hydrocodone Bitartrate and Aspirin Tablets, like other opioids, can be diverted for nonmedical use into illicit channels of distribution. Careful record-keeping of prescribing information, including quantity, frequency, and renewal requests, as required by state and federal law, is strongly advised.

Proper assessment of the patient, proper prescribing practices, periodic reevaluation of therapy, and proper dispensing and storage are appropriate measures that help to limit abuse of opioid drugs.

Risks Specific to Abuse of Hydrocodone Bitartrate and Aspirin Tablets

Abuse of Hydrocodone Bitartrate and Aspirin Tablets poses a risk of overdose and death. The risk is increased with concurrent abuse of Hydrocodone Bitartrate and Aspirin Tablets with alcohol and/or other CNS depressants.

Parenteral drug abuse is commonly associated with transmission of infectious diseases such as hepatitis and HIV.

Dependence

Both tolerance and physical dependence can develop during use of opioid therapy.

Tolerance is a physiological state characterized by a reduced response to a drug after repeated administration (i.e., a higher dose of a drug is required to produce the same effect that was once obtained at a lower dose).

Physical dependence is a state that develops as a result of physiological adaptation in response to repeated drug use, manifested by withdrawal signs and symptoms after abrupt discontinuation or a significant dose reduction of a drug.

Withdrawal may be precipitated through the administration of drugs with opioid antagonist activity (e.g., naloxone), mixed agonist/antagonist analgesics (e.g., pentazocine, butorphanol, nalbuphine), or partial agonists (e.g., buprenorphine). Physical dependence may not occur to a clinically significant degree until after several days to weeks of continued use.

Do not abruptly discontinue Hydrocodone Bitartrate and Aspirin Tablets in a patient physically dependent on opioids. Rapid tapering of Hydrocodone Bitartrate and Aspirin Tablets in a patient physically dependent on opioids may lead to serious withdrawal symptoms, uncontrolled pain, and suicide. Rapid discontinuation has also been associated with attempts to find other sources of opioid analgesics, which may be confused with drug-seeking for abuse.

When discontinuing Hydrocodone Bitartrate and Aspirin Tablets, gradually taper the dosage using a patient-specific plan that considers the following: the dose of Hydrocodone Bitartrate and Aspirin Tablets the patient has been taking, the duration of treatment, and the physical and psychological attributes of the patient. To improve the likelihood of a successful taper and minimize withdrawal symptoms, it is important that the opioid tapering schedule is agreed upon by the patient. In patients taking opioids for an extended period of time at high doses, ensure that a multimodal approach to pain management, including mental health support (if needed), is in place prior to initiating an opioid analgesic taper [see DOSAGE AND ADMINISTRATION, and WARNINGS].

Infants born to mothers physically dependent on opioids will also be physically dependent and may exhibit respiratory difficulties and withdrawal signs [see Pregnancy].

OVERDOSAGE

Clinical Presentation

Acute overdose with Hydrocodone Bitartrate and Aspirin Tablets can be manifested by respiratory depression, somnolence progressing to stupor or coma, skeletal muscle flaccidity, cold and clammy skin, constricted pupils, and, in some cases, pulmonary edema, bradycardia, hypotension, hypoglycemia, partial or complete airway obstruction, atypical snoring, and death. Marked mydriasis rather than miosis may be seen with hypoxia in overdose situations.

Early signs of acute aspirin (salicylate) overdose including tinnitus occur at plasma concentrations approaching 200 mcg/mL. Plasma concentrations of aspirin above 300 mcg/mL are toxic. Severe toxic effects are associated with levels above 400 mcg/mL. A single lethal dose of aspirin in adults is not known with certainty but death may be expected at 30 g. For real or suspected overdose, a Poison Control Center should be contacted immediately.

In acute salicylate overdose, severe acid-base and electrolyte disturbances may occur and are complicated by hyperthermia and dehydration, and coma. Respiratory alkalosis occurs early while hyperventilation is present, but is quickly followed by metabolic acidosis. Serious symptoms such as depression, coma, and respiratory failure progress rapidly.

Salicylism (chronic salicylate toxicity) may be noted by symptoms such as dizziness, tinnitus, difficulty hearing, nausea, vomiting, diarrhea, and mental confusion. More severe salicylism may result in respiratory alkalosis.

Treatment of Overdose

In case of overdose, priorities are the reestablishment of a patent and protected airway and institution of assisted or controlled ventilation, if needed. Employ other supportive measures (including oxygen and vasopressors) in the management of circulatory shock and pulmonary edema as indicated. Cardiac arrest or arrhythmias will require advanced life-support measures.

Opioid antagonists, such as naloxone or nalmefene, are specific antidotes to respiratory depression resulting from opioid overdose. For clinically significant respiratory or circulatory depression secondary opioid overdose, administer an opioid antagonist. Because the duration of opioid reversal is expected to be less than the duration of action of hydrocodone in Hydrocodone Bitartrate and Aspirin Tablets, carefully monitor the patient until spontaneous respiration is reliably re-established. If the response to an opioid antagonist is suboptimal or only brief in nature, administer additional antagonist as directed by the product’s prescribing information.

In an individual physically dependent on opioids, administration of the recommended usual dosage of the antagonist will precipitate an acute withdrawal syndrome. The severity of the withdrawal symptoms experienced will depend on the degree of the physical dependence and the dose of the antagonist administered. If a decision is made to treat serious respiratory depression in the physically dependent patient, administration of the antagonist should be begun with care and by titration with smaller than usual doses of the antagonist.

In severe cases of salicylate overdose, hyperthermia and hypovolemia are the major immediate threats to life. Children should be sponged with tepid water. Replacement fluid should be administered intravenously and augmented with correction of acidosis. Plasma electrolytes and pH should be monitored to promote alkaline diuresis of salicylate if renal function is normal. Infusion of glucose may be required to control hypoglycemia. With more severe acute toxicity respiratory alkalosis may occur.

Hemodialysis and peritoneal dialysis can be performed to reduce the body content of aspirin. In patients with renal insufficiency or in cases of life-threatening salicylate intoxication dialysis is usually required. Exchange transfusion may be indicated in infants and young children.

DOSAGE AND ADMINISTRATION

Important Dosage and Administration Instructions

Hydrocodone Bitartrate and Aspirin Tablets should be prescribed only by healthcare professionals who are knowledgeable about the use of opioids and how to mitigate the associated risks.

Use the lowest effective dosage for the shortest duration of time consistent with the individual patient treatment goals [see WARNINGS]. Because the risk of overdose increases as opioid doses increase, reserve titration to higher doses of Hydrocodone Bitartrate with Aspirin Tablets for patients in whom lower doses are insufficiently effective and in whom the expected benefits of using higher dose opioid clearly outweigh the substantial risks.

Many acute pain conditions (e.g., the pain that occurs with a number of surgical procedures or acute musculoskeletal injuries) require no more than a few days of an opioid analgesic. Clinical guidelines on opioid prescribing for some acute pain conditions are available.

There is variability in the opioid analgesic dose and duration needed to adequately manage pain due both to the cause of pain and to individual patient factors. Initiate the dosing regimen for each patient individually, taking into account the patient’s underlying cause and severity of pain, prior analgesic treatment and response, and risk factors for addition, abuse, and misuse [see WARNINGS].

Respiratory depression can occur at any time during opioid therapy, especially when initiating and following dosage increase with Hydrocodone Bitartrate and Aspirin Tablets. Consider the risk when selecting an initial dose and when making dose adjustments [see WARNINGS]. Administer Hydrocodone Bitartrate and Aspirin Tablets with food or a full glass of water to minimize GI distress.

Patient Access to Naloxone for the Emergency Treatment of Opioid Overdose

- Discuss the availability of naloxone for the emergency treatment of opioid overdose with the patient and caregiver and assess the potential need for access to naloxone, both when initiating and renewing treatment with Hydrocodone Bitartrate and Aspirin Tablets [see WARNINGS; Life-Threatening Respiratory Depression, PRECAUTIONS; Information for Patients/Caregivers].
- Inform patients and caregivers about the various ways to obtain naloxone as permitted by individual state naloxone dispensing and prescribing requirements or guidelines (e.g., by prescription, directly from a pharmacist, or as part of a community-based program).
- Consider prescribing naloxone, based on the patient’s risk factors for overdose, such as concomitant use of CNS depressants, a history of opioid use disorder, or prior opioid overdose. The presence of risk factors for overdose should not prevent the proper management of pain in any given patient [see WARNINGS; Addiction, Abuse, and Misuse; Life-Threatening Respiratory Depression; Life-Threatening Respiratory Depression; Risks from Concomitant Use with Benzodiazepines or Other CNS Depressants].
- Consider prescribing naloxone when there are household members (including children) or other close contacts at risk for accidental ingestion or overdose.

Initial Dosage

Initiating Treatment with Hydrocodone Bitartrate and Aspirin Tablets

Initiate treatment with Hydrocodone Bitartrate and Aspirin Tablets using one (1) or two (2) tablets every four (4) to six (6) hours, as needed for pain at the lowest dose necessary to achieve adequate analgesia. Titrate the dose based upon the individual patient’s response to their initial dose of Hydrocodone Bitartrate and Aspirin Tablets.

Conversion from Other Opioids to Hydrocodone Bitartrate and Aspirin Tablets

There is inter-patient variability in the potency of opioid drugs and opioid formulations. Therefore, a conservative approach is advised when determining the total daily dosage of Hydrocodone Bitartrate and Aspirin Tablets. It is safer to underestimate a patient’s 24-hour Hydrocodone Bitartrate and Aspirin Tablets dosage than to overestimate the 24-hour Hydrocodone Bitartrate and Aspirin Tablets dosage and manage an adverse reaction due to an overdose.

Conversion from Hydrocodone Bitartrate and Aspirin Tablets to Extended-Release Hydrocodone

The relative bioavailability of Hydrocodone Bitartrate and Aspirin Tablets compared to extended-release hydrocodone is unknown, so conversion to extended-release hydrocodone may lead to increased risk of excessive sedation and respiratory depression.

Titration and Maintenance of Therapy

Individually titrate Hydrocodone Bitartrate and Aspirin Tablets to a dose that provides adequate analgesia and minimizes adverse reactions. Continually reevaluate patients receiving Hydrocodone Bitartrate and Aspirin Tablets to assess the maintenance of pain control, signs and symptoms of opioid withdrawal, and other adverse reactions, as well as reassess for the development of addiction, abuse, or misuse [see WARNINGS]. Frequent communication is important among the prescriber, other members of the healthcare team, the patient, and the caregiver/family during periods of changing analgesic requirements, including initial titration.

If the level of pain increases after dosage stabilization, attempt to identify the source of the increased pain before increasing the Hydrocodone Bitartrate and Aspirin Tablets dosage. If after increasing the dosage, unacceptable opioid-related adverse reactions are observed (including an increase in pain after dosage increase), consider reducing the dosage [see WARNINGS]. Adjust the dosage to obtain an appropriate balance between management of pain and opioid-related adverse reactions.

Safe Reduction or Discontinuation of Hydrocodone Bitartrate and Aspirin Tablets

Do not abruptly discontinue Hydrocodone Bitartrate and Aspirin Tablets in patients who may be physically dependent on opioids. Rapid discontinuation of opioid analgesics in patients who are physically dependent on opioids has resulted in serious withdrawal symptoms, uncontrolled pain, and suicide. Rapid discontinuation has also been associated with attempts to find other sources of opioid analgesics, which may be confused with drug-seeking for abuse. Patients may also attempt to treat their pain or withdrawal symptoms with illicit opioids, such as heroin, and other substances.

When a decision has been made to decrease the dose or discontinue therapy in an opioid-dependent patient taking Hydrocodone Bitartrate and Aspirin Tablets, there are a variety of factors that should be considered, including the total daily dose of opioid (including Hydrocodone Bitartrate and Aspirin Tablets) the patient has been taking, the duration of treatment, the type of pain being treated, and the physical and psychological attributes of the patient. It is important to ensure ongoing care of the patient and to agree on an appropriate tapering schedule and follow-up plan so that patient and provider goals and expectations are clear and realistic. When opioid analgesics are being discontinued due to a suspected substance use disorder, evaluate and treat the patient, or refer for evaluation and treatment of the substance use disorder. Treatment should include evidence-based approaches, such as medication assisted treatment of opioid use disorder. Complex patients with co-morbid pain and substance use disorders may benefit from referral to a specialist.

There are no standard opioid tapering schedules that are suitable for all patients. Good clinical practice dictates a patient-specific plan to taper the dose of the opioid gradually. For patients on Hydrocodone Bitartrate and Aspirin Tablets who are physically opioid-dependent, initiate the taper by a small enough increment (e.g., no greater than 10% to 25% of the total daily dose) to avoid withdrawal symptoms, and proceed with dose-lowering at an interval of every 2 to 4 weeks. Patients who have been taking opioids for briefer periods of time may tolerate a more rapid taper.

It may be necessary to provide the patient with lower dosage strengths to accomplish a successful taper. Reassess the patient frequently to manage pain and withdrawal symptoms, should they emerge. Common withdrawal symptoms include restlessness, lacrimation, rhinorrhea, yawning, perspiration, chills, myalgia, and mydriasis. Other signs and symptoms also may develop, including irritability, anxiety, backache, joint pain, weakness, abdominal cramps, insomnia, nausea, anorexia, vomiting, diarrhea, or increased blood pressure, respiratory rate, or heart rate. If withdrawal symptoms arise, it may be necessary to pause the taper for a period of time or raise the dose of the opioid analgesic to the previous dose, and then proceed with a slower taper. In addition, evaluate patients for any changes in mood, emergence of suicidal thoughts, or use of other substances.

When managing patients taking opioid analgesics, particularly those who have been treated for an extended period of time, and/or with high doses for chronic pain, ensure that a multimodal approach to pain management, including mental health support (if needed), is in place prior to initiating an opioid analgesic taper. A multimodal approach to pain management may optimize the treatment of chronic pain, as well as assist with the successful tapering of the opioid analgesic [see WARNINGS; Withdrawal, DRUG ABUSE AND DEPENDENCE].

HOW SUPPLIED

Hydrocodone Bitartrate and Aspirin Tablets are supplied as oval, bisected white tablets containing 5 mg Hydrocodone Bitartrate and 500 mg of Aspirin. Each tablet is debossed with “MLB” bisect “125” on one side and “5-500” on the other side.

Bottles of 100 tablets – NDC 79739-7182-1

Store at 25°C (77°F); excursions permitted to 15°-30°C (59°-86°F). [See USP Controlled Room Temperature].

Dispense in a tight, light-resistant container as defined in the USP, with a child-resistant closure (as required).

Protect from moisture.

Store Hydrocodone Bitartrate and Aspirin Tablets securely and dispose of properly [see PRECAUTIONS; Information for Patients/Caregivers]

Manufactured by: LGM Pharma Solutions, LLC, Irvine, CA 92614

7182-PD

Rev 01/2024

Medication Guide

Hydrocodone Bitartrate (hye” droe koe’ done bye tar’ trate) and Aspirin (as’ pir in) Tablets CII

Hydrocodone Bitartrate and Aspirin Tablets are:

- A strong prescription pain medicine that contains an opioid (narcotic) that is used to manage pain severe enough to require an opioid pain medicine, when other pain treatments such as non-opioid pain medicines do not treat your pain well enough or you cannot tolerate them.
- An opioid pain medicine that can put you at risk for overdose and death. Even if you take your dose correctly as prescribed you are at risk for opioid addiction, abuse, and misuse that can lead to death.

Important information about Hydrocodone Bitartrate and Aspirin Tablets:

- Get emergency help right away or call 911 if you take too much Hydrocodone Bitartrate and Aspirin Tablets (overdose). When you first start taking Hydrocodone Bitartrate and Aspirin Tablets, when your dose is changed, or if you take too much (overdose), serious or life-threatening breathing problems that can lead to death may occur. Talk to your healthcare provider about naloxone, a medicine for the emergency treatment of an opioid overdose.
- Taking Hydrocodone Bitartrate and Aspirin Tablets with other opioid medicines, benzodiazepines, alcohol, or other central nervous system depressants (including street drugs) can cause severe drowsiness, decreased awareness, breathing problems, coma, and death.
- Never give anyone else your Hydrocodone Bitartrate and Aspirin Tablets. They could die from taking it. Selling or giving away Hydrocodone Bitartrate and Aspirin Tablets is against the law.
- Store Hydrocodone Bitartrate and Aspirin Tablets securely, out of sight and reach of children, and in a location not accessible by others, including visitors to the home.
- Increases risk of bleeding and ulcers.

Do not take Hydrocodone Bitartrate and Aspirin Tablets if you have:

- severe asthma, asthma in combination with runny nose and nasal polyps, trouble breathing, or other lung problems.
- a bowel blockage or have narrowing of the stomach or intestines.
- known hypersensitivity to hydrocodone or aspirin, or any ingredient in Hydrocodone Bitartrate and Aspirin Tablets.
- known allergy to nonsteroidal anti-inflammatory drug products (NSAIDs)
- a rare disorder in which your blood doesn’t clot normally (hemophilia)

Do not give Hydrocodone Bitartrate and Aspirin Tablets to a child or teenager with a viral illness. Reye’s syndrome, a life-threatening condition, can happen when aspirin (an ingredient in Hydrocodone Bitartrate and Aspirin Tablets) is used in children and teenagers who have certain viral illnesses.

Before taking Hydrocodone Bitartrate and Aspirin Tablets, tell your healthcare provider if you have a history of:

- head injury, seizures
- liver, kidney, thyroid problems
- problems urinating
- pancreas or gallbladder problems
- abuse of street or prescription drugs, alcohol addiction, opioid overdose, or mental health problems.
- stomach ulcers, or stomach or intestinal bleeding with use of acetylsalicylic acid (ASA) or NSAIDs

Tell your healthcare provider if you are:

- noticing your pain getting worse. If your pain gets worse after you take Hydrocodone Bitartrate and Aspirin Tablets, do not take more of Hydrocodone Bitartrate and Aspirin Tablets without first talking to your healthcare provider. Talk to your healthcare provider if the pain that you have increases, if you feel more sensitive to pain, or if you have new pain after taking Hydrocodone Bitartrate and Aspirin Tablets.
- pregnant or planning to become pregnant. Use of Hydrocodone Bitartrate and Aspirin Tablets for extended period of time during pregnancy can cause withdrawal symptoms in your newborn baby that could be life-threatening if not recognized and treated. Taking NSAID-containing products like Hydrocodone Bitartrate and Aspirin Tablets at about 20 weeks of pregnancy or later may harm your unborn baby. If you need to take NSAIDs for more than 2 days when you are between 20 and 30 weeks of pregnancy, your healthcare provider may need to monitor the amount of fluid in your womb around your baby. You should not take NSAIDs after about 30 weeks of pregnancy.
- breastfeeding. Hydrocodone bitartrate and aspirin passes into breast milk and may harm your baby. Carefully observe infants for increased sleepiness (more than usual), breathing difficulties, or limpness. Seek immediate medical care if you notice these signs.
- develop any type of rash or fever. Contact your healthcare provider as soon as possible and stop taking Hydrocodone Bitartrate and Aspirin Tablets.

- living in a household where there are small children or someone who has abused street or prescription drugs
- taking prescription or over-the-counter medicines, vitamins, or herbal supplements. Taking Hydrocodone Bitartrate and Aspirin Tablets with certain other medicines can cause serious side effects that could lead to death. Taking with corticosteroids or anticoagulants increases risk of ulcers and stomach/intestinal bleeding.

When taking Hydrocodone Bitartrate and Aspirin Tablets:

- Do not change your dose. Take Hydrocodone Bitartrate and Aspirin Tablets exactly as prescribed by your healthcare provider. Use the lowest dose possible for the shortest time needed.
- For acute (short-term) pain, you may only need to take Hydrocodone Bitartrate and Aspirin Tablets for a few days. You may have some Hydrocodone Bitartrate and Aspirin Tablets left over that you did not use. See disposal information at the bottom of this section for directions on how to safely throw away (dispose of) your unused Hydrocodone Bitartrate and Aspirin Tablets.
- Take your prescribed dose every four to six hours as needed for pain.
- Do not take more than your prescribed dose. If you miss a dose, take your next dose at your usual time.
- Call your healthcare provider if the dose you are taking does not control your pain.
- If you have been taking Hydrocodone Bitartrate and Aspirin Tablets regularly, do not stop taking Hydrocodone Bitartrate and Aspirin Tablets without talking to your healthcare provider.
- Dispose of expired, unwanted, or unused Hydrocodone Bitartrate and Aspirin Tablets by promptly flushing down the toilet, if a drug take-back option is not readily available. Visit www.fda.gov/drugdisposal for additional information on disposal of unused medicines.

While taking Hydrocodone Bitartrate and Aspirin Tablets DO NOT:

- Drive or operate heavy machinery, until you know how Hydrocodone Bitartrate and Aspirin Tablets affects you. Hydrocodone Bitartrate and Aspirin Tablets can make you sleepy, dizzy, or lightheaded.
- Drink alcohol or use prescription or over-the-counter medicines that contain alcohol. Using products containing alcohol during treatment with Hydrocodone Bitartrate and Aspirin Tablets may cause you to overdose and die.

The possible side effects of Hydrocodone Bitartrate and Aspirin Tablets:

- Bleeding, constipation, nausea, sleepiness, vomiting, tiredness, headache, dizziness, abdominal pain, rash, or fever. Call your healthcare provider if you have any of these symptoms and they are severe.
- trouble breathing, shortness of breath, fast heartbeat, chest pain, swelling of your face, tongue, or throat, extreme drowsiness, light-headedness when changing positions, feeling faint, agitation, high body temperature, trouble walking, stiff muscles, or mental changes such as confusion.

Get emergency medical help or call 911 right away if you have:

These are not all the possible side effects of Hydrocodone Bitartrate and Aspirin Tablets. Call your healthcare provider for medical advice about side effects. You may report side effects to FDA at 1-800-FDA-1088. For more information go to dailymed.nlm.nih.gov.

Manufactured by:
LGM Pharma Solutions, LLC
Irvine, CA 92614

This Medication Guide has been approved by the U.S. Food and Drug Administration.

7182-PD

Issued: 01/2024

PRINCIPAL DISPLAY PANEL

NDC 79739-7182-1

Hydrocodone Bitartrate and Aspirin Tablets CIII

5 mg/500 mg

PHARMACIST: Dispense the Medication Guide provided separately to each patient.

Rx only 100 TABLETS

Manufactured by : LGM Pharma Solutions, LLC

Irvine, CA 92614

EACH TABLET CONTAINS:

Hydrocodone Bitartrate ………………………. 5 mg
Aspirin………………………………………………. 500 mg

Store at 25°C (77°F); excursions permitted to 15°-30°C (59°-86°F). [See USP Controlled Room Temperature].

Dispense in a tight, light-resistant containers as defined in the USP, with a child-resistant closure (as required).

Protect from moisture.

7182-PD Rev 05/2021

The usual adult dosage is one or two tablets every four to six hours as needed for pain.

KEEP OUT OF THE REACH OF CHILDREN.